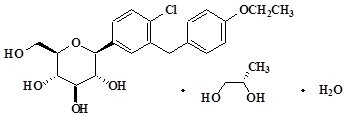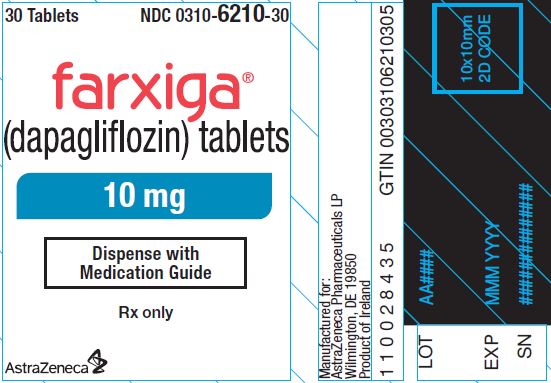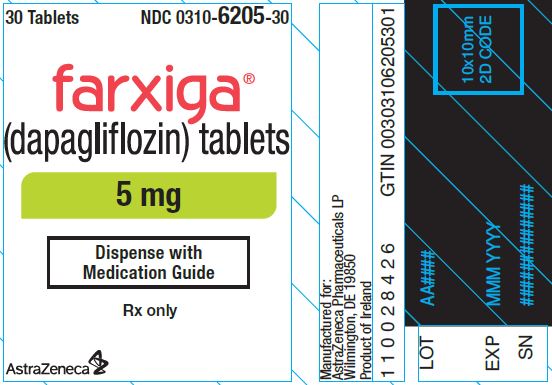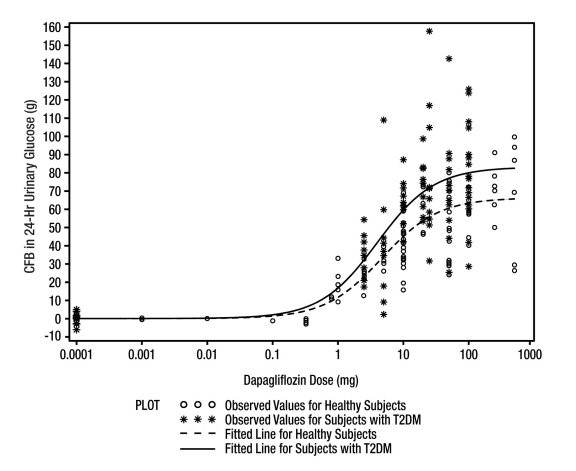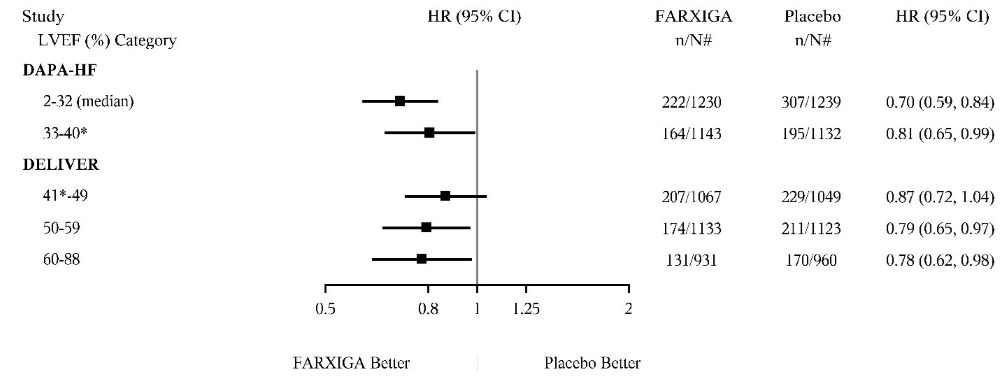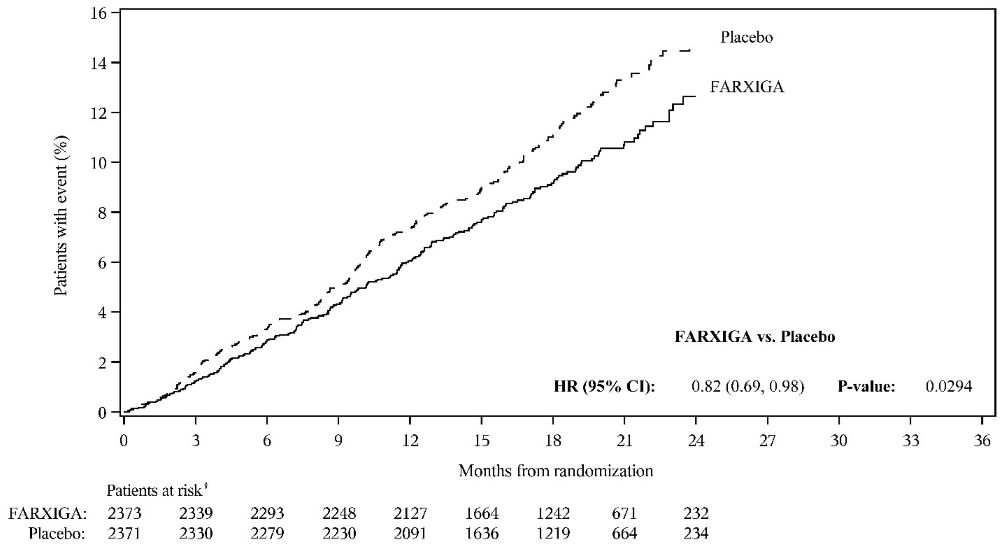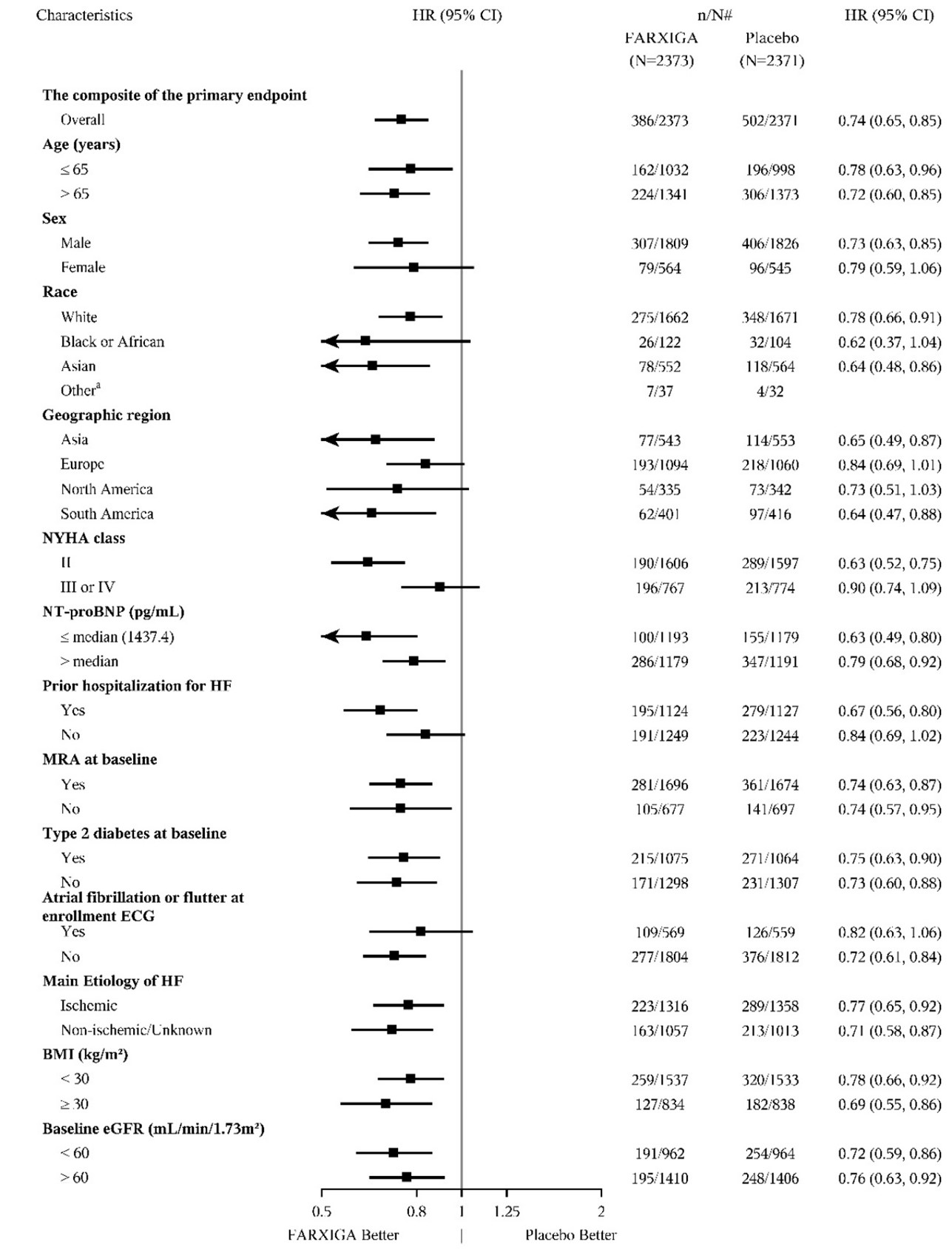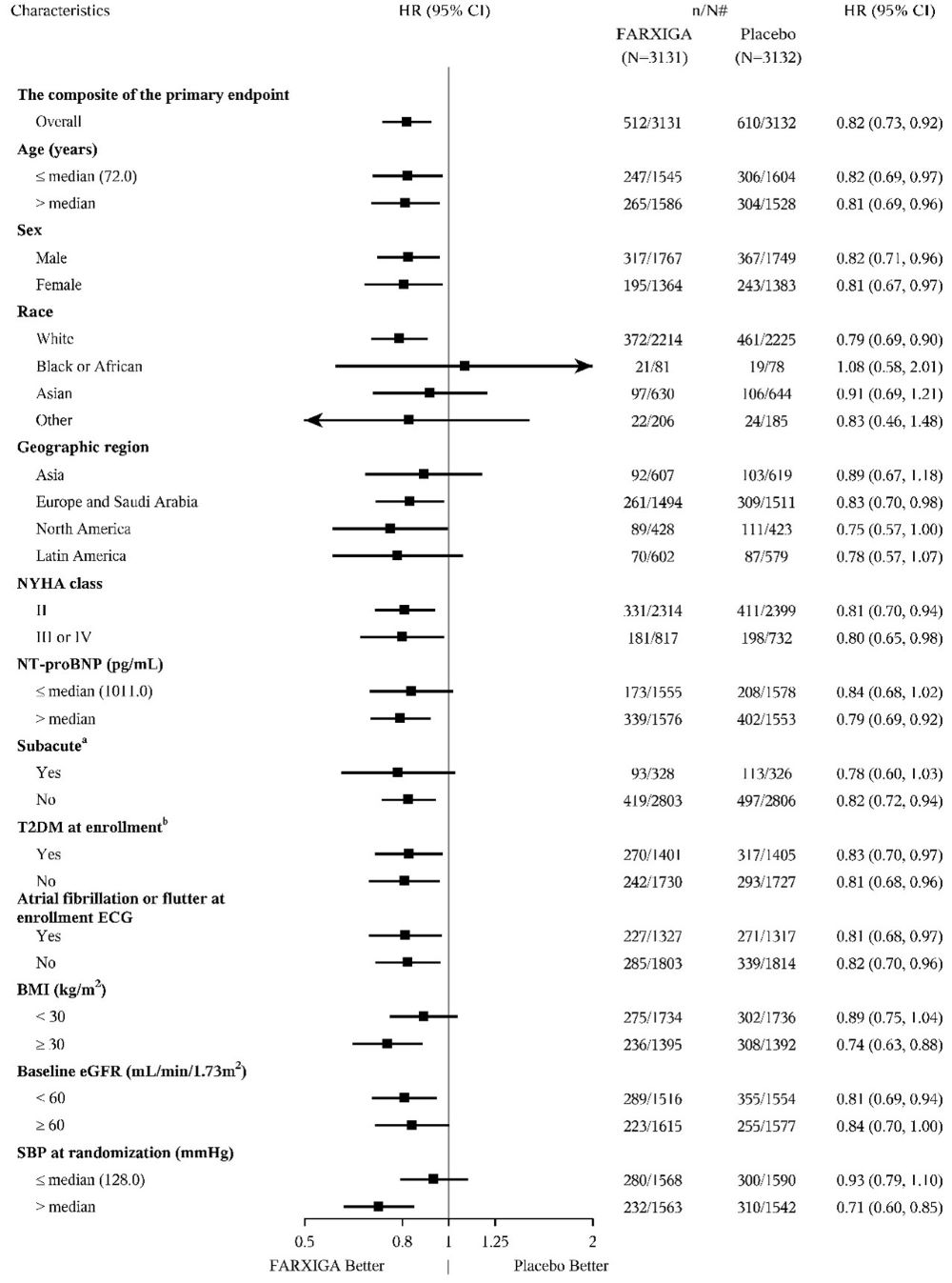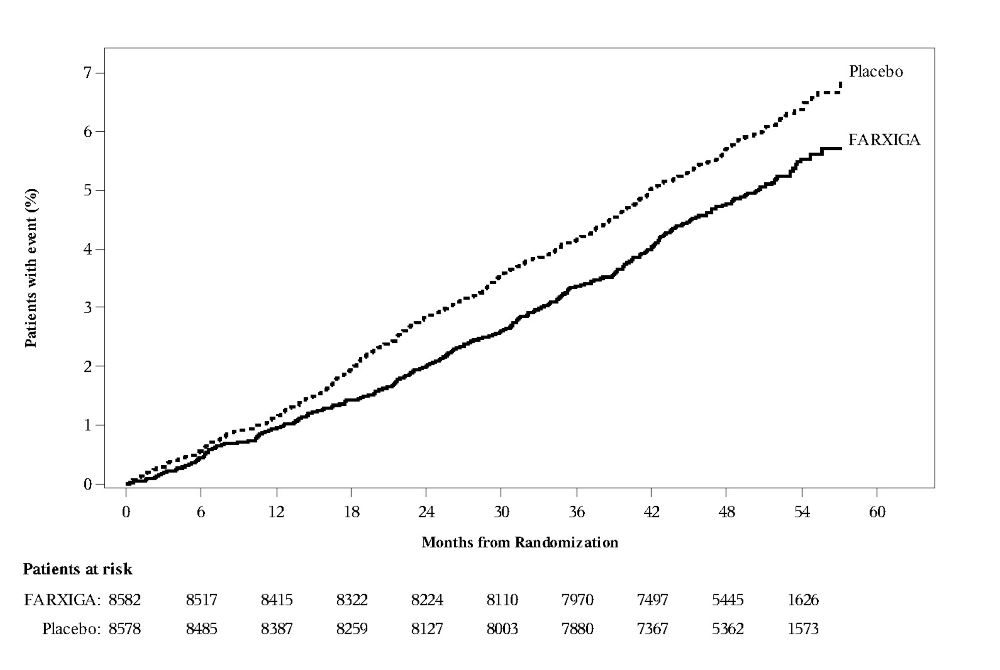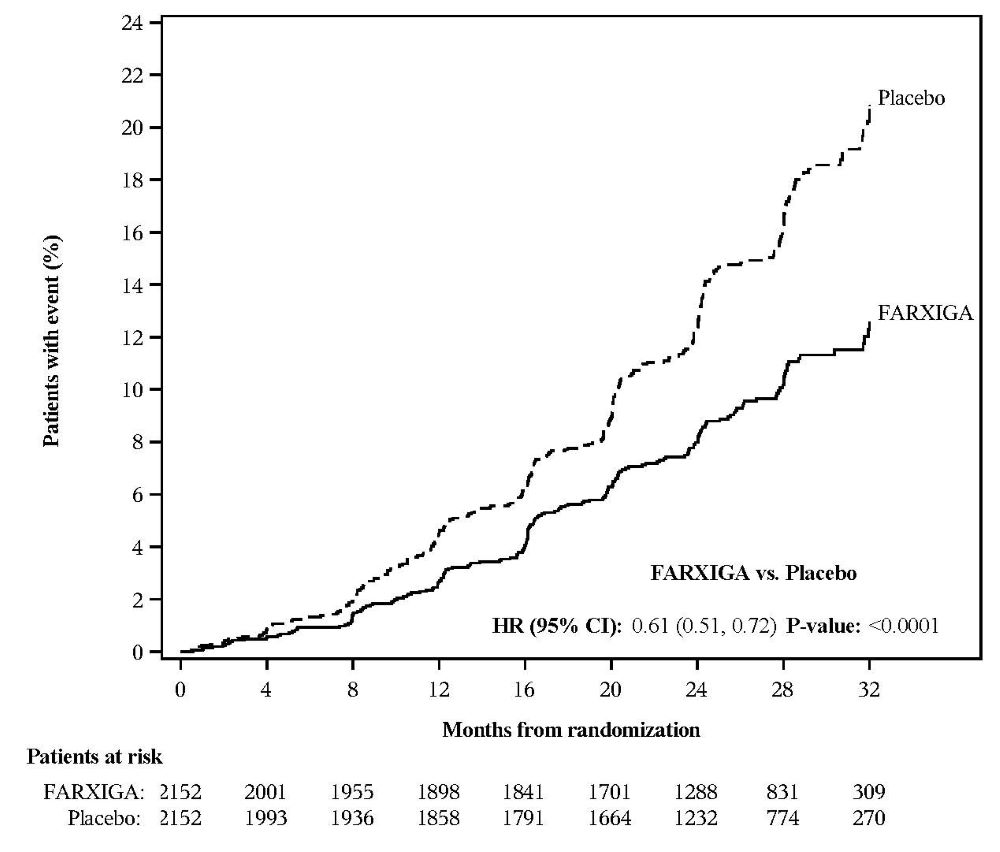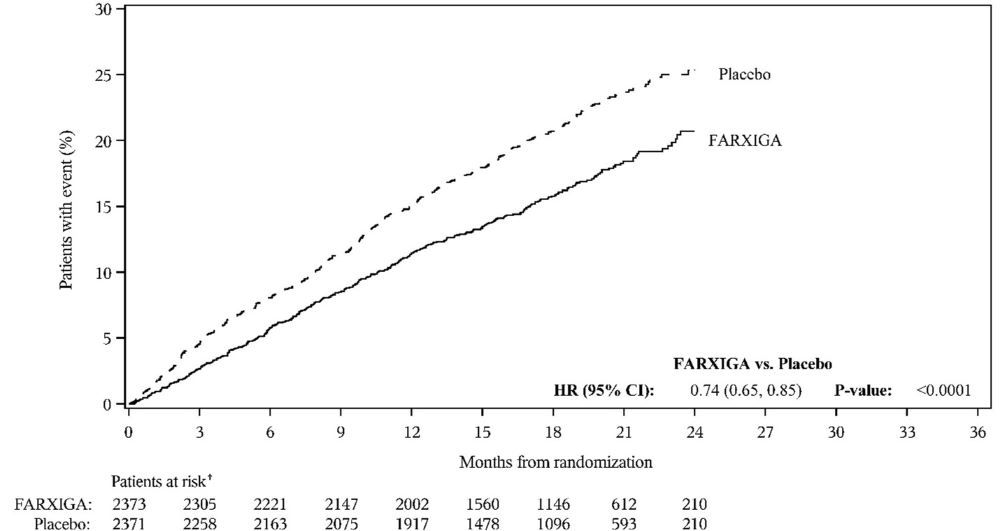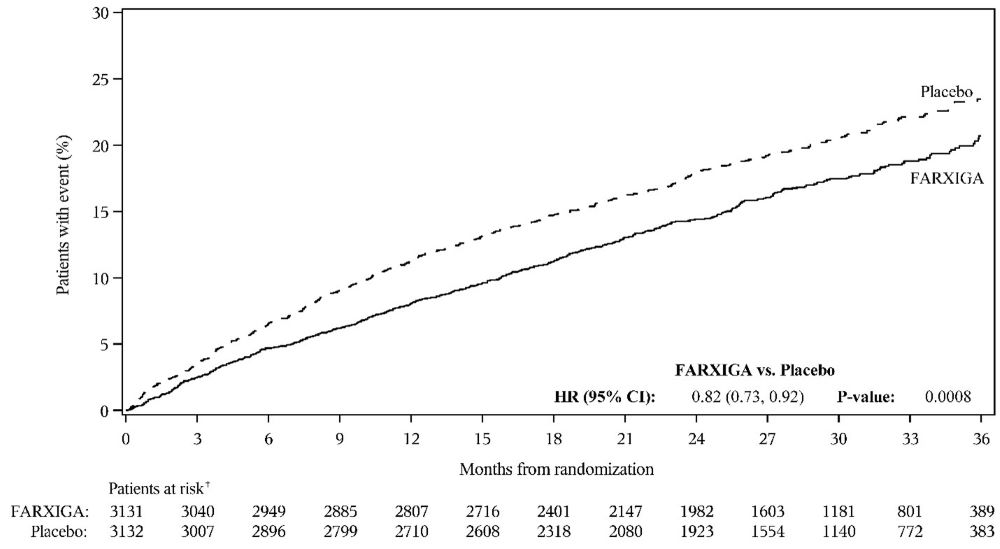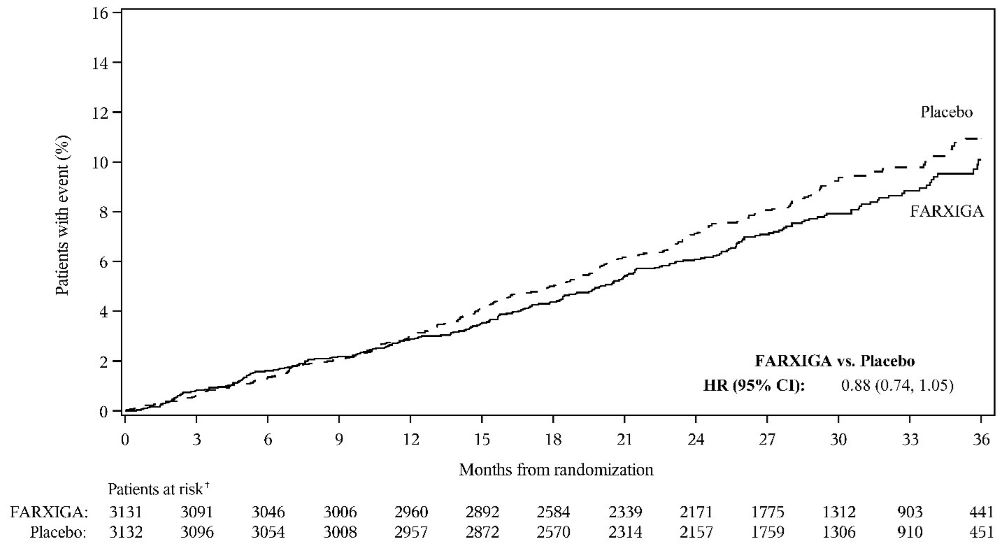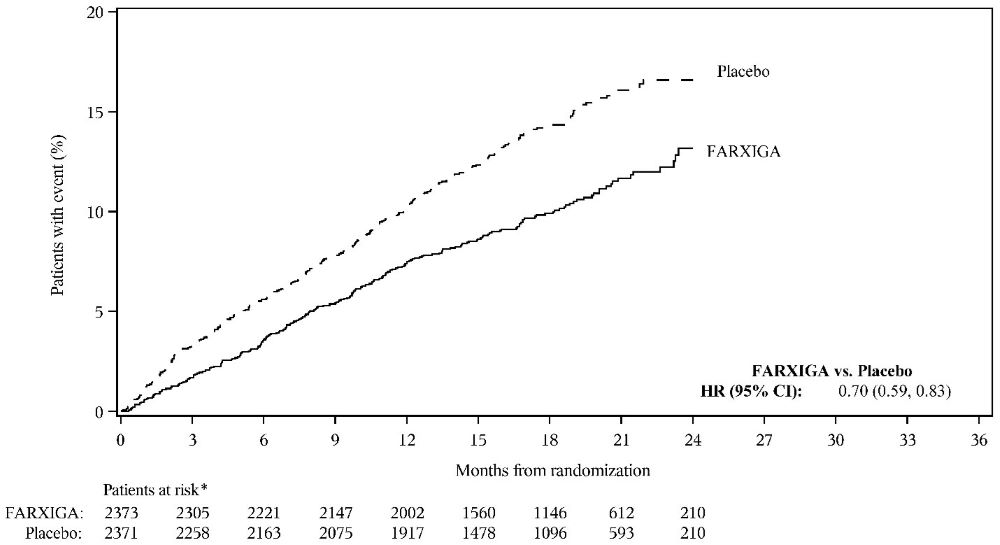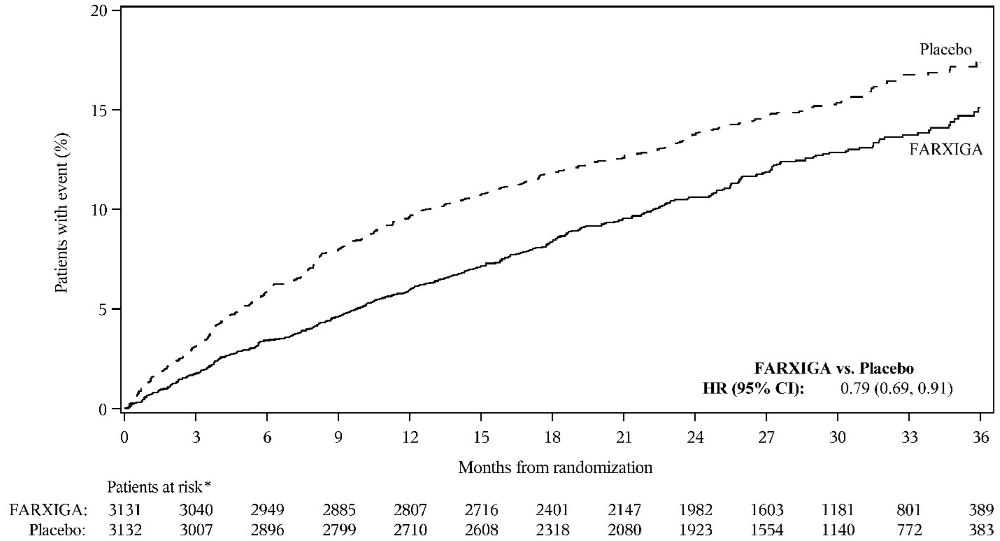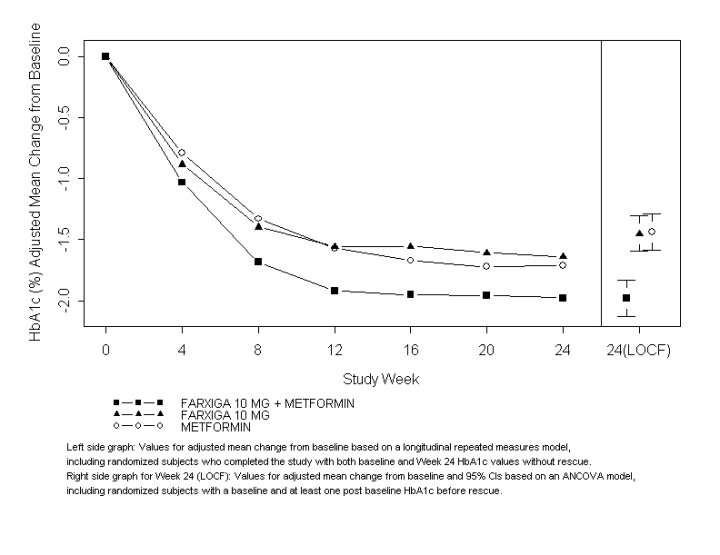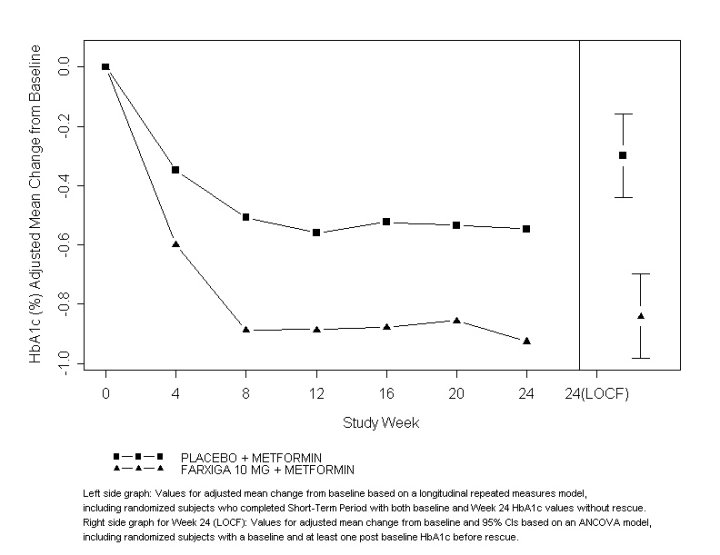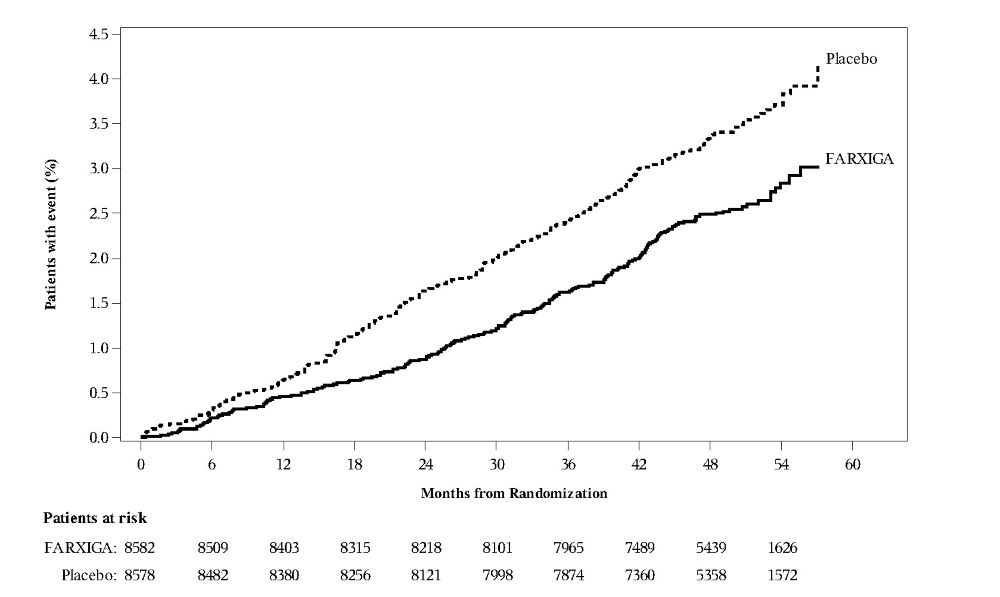 DRUG LABEL: FARXIGA
NDC: 0310-6205 | Form: TABLET, FILM COATED
Manufacturer: AstraZeneca Pharmaceuticals LP
Category: prescription | Type: HUMAN PRESCRIPTION DRUG LABEL
Date: 20251222

ACTIVE INGREDIENTS: DAPAGLIFLOZIN PROPANEDIOL 5 mg/1 1
INACTIVE INGREDIENTS: MICROCRYSTALLINE CELLULOSE; anhydrous lactose; CROSPOVIDONE, UNSPECIFIED; silicon dioxide; magnesium stearate

HIGHLIGHTS OF PRESCRIBING INFORMATION

These highlights do not include all the information needed to use FARXIGA safely and effectively. See full prescribing information for FARXIGA.
FARXIGA® (dapagliflozin) tablets, for oral use
Initial U.S. Approval: 2014

RECENT MAJOR CHANGES

Indications and Usage (1) 06/2024

Dosage and Administration (2.2) 06/2024

1 INDICATIONS AND USAGE

FARXIGA is a sodium-glucose cotransporter 2 (SGLT2) inhibitor indicated:

- To reduce the risk of sustained eGFR decline, end-stage kidney disease, cardiovascular death, and hospitalization for heart failure in adults with chronic kidney disease at risk of progression.. (1)
- To reduce the risk of cardiovascular death, hospitalization for heart failure, and urgent heart failure visit in adults with heart failure (1)
- To reduce the risk of hospitalization for heart failure in adults with type 2 diabetes mellitus and either established cardiovascular disease or multiple cardiovascular risk factors. (1)
- As an adjunct to diet and exercise to improve glycemic control in adults and pediatric patients aged 10 years and older with type 2 diabetes mellitus. (1)

Limitations of use:

- Not recommended for use to improve glycemic control in patients with type 1 diabetes mellitus. (1)
- Not recommended for use to improve glycemic control in patients with type 2 diabetes mellitus with an eGFR less than 45 mL/min/1.73 m^2. FARXIGA is likely to be ineffective in this setting based upon its mechanism of action. (1)
- Not recommended for the treatment of chronic kidney disease in patients with polycystic kidney disease or patients requiring or with a recent history of immunosuppressive therapy for the treatment of kidney disease. FARXIGA is not expected to be effective in these populations. (1)

2 DOSAGE AND ADMINISTRATION

- Assess renal function prior to initiation and then as clinically indicated. Assess volume status and correct volume depletion before initiating. (2.1)
- To improve glycemic control, the recommended starting dose is 5 mg orally once daily. Dosage can be increased to 10 mg orally once daily for additional glycemic control. (2.2)
- For all other indications, the recommended dosage is 10 mg orally once daily. (2.2)
- See full prescribing information for dosage recommendations in patients with renal impairment. (2.2, 2.3)
- Withhold FARXIGA for at least 3 days, if possible, prior to major surgery or procedures associated with prolonged fasting. (2.3)

3 DOSAGE FORMS AND STRENGTHS

Tablets: 5 mg and 10 mg (3)

4 CONTRAINDICATIONS

- History of serious hypersensitivity reaction to dapagliflozin or any of the excipients in FARXIGA. (4)

5 WARNINGS AND PRECAUTIONS

- Diabetic Ketoacidosis in Patients with Type 1 Diabetes Mellitus and Other Ketoacidosis: Consider ketone monitoring in patients with type 1 diabetes mellitus and consider ketone monitoring in others at risk for ketoacidosis, as indicated. Assess for ketoacidosis regardless of presenting blood glucose levels and discontinue FARXIGA if ketoacidosis is suspected. Monitor patients for resolution of ketoacidosis before restarting. (5.1)
- Volume depletion: Before initiating FARXIGA, assess volume status and renal function in the elderly, patients with renal impairment or low systolic blood pressure, and in patients on diuretics. Monitor for signs and symptoms during therapy. (5.2)
- Urosepsis and Pyelonephritis: Evaluate for signs and symptoms of urinary tract infections and treat promptly, if indicated. (5.3)
- Hypoglycemia: Consider a lower dose of insulin or the insulin secretagogue to reduce the risk of hypoglycemia when used in combination with FARXIGA. (5.4)
- Necrotizing Fasciitis of the Perineum (Fournier’s Gangrene): Serious, life-threatening cases have occurred in patients with diabetes, both females and males. Assess patients presenting with pain or tenderness, erythema, or swelling in the genital or perineal area, along with fever or malaise. If suspected, institute prompt treatment. (5.5)
- Genital Mycotic Infections: Monitor and treat if indicated. (5.6)

6 ADVERSE REACTIONS

- Most common adverse reactions (5% or greater incidence) were female genital mycotic infections, nasopharyngitis, and urinary tract infections. (6.1)

To report SUSPECTED ADVERSE REACTIONS, contact AstraZeneca at 1-800-236-9933 or FDA at 1-800-FDA-1088 or www.fda.gov/medwatch.

7 DRUG INTERACTIONS

- See full prescribing information for information on drug interactions and interference of FARXIGA with laboratory tests. (7)

8 USE IN SPECIFIC POPULATIONS

- Pregnancy: Advise females of the potential risk to a fetus especially during the second and third trimesters. (8.1)
- Lactation: Not recommended when breastfeeding. (8.2)
- Geriatrics: Higher incidence of adverse reactions related to hypotension. (8.5)
- Renal Impairment: Higher incidence of adverse reactions related to volume depletion. (8.6)

FULL PRESCRIBING INFORMATION

1 INDICATIONS AND USAGE

FARXIGA (dapagliflozin) is indicated:

- To reduce the risk of sustained eGFR decline, end-stage kidney disease, cardiovascular death, and hospitalization for heart failure in adults with chronic kidney disease at risk of progression.
- To reduce the risk of cardiovascular death, hospitalization for heart failure, and urgent heart failure visit in adults with heart failure.
- To reduce the risk of hospitalization for heart failure in adults with type 2 diabetes mellitus and either established cardiovascular disease or multiple cardiovascular risk factors.
- As an adjunct to diet and exercise to improve glycemic control in adults and pediatric patients aged 10 years and older with type 2 diabetes mellitus.

Limitations of Use

- FARXIGA is not recommended for use to improve glycemic control in patients with type 1 diabetes mellitus [see Warnings and Precautions (5.1)].
- FARXIGA is not recommended for use to improve glycemic control in patients with type 2 diabetes mellitus with an eGFR less than 45 mL/min/1.73 m^2. FARXIGA is likely to be ineffective in this setting based upon its mechanism of action.
- FARXIGA is not recommended for the treatment of chronic kidney disease in patients with polycystic kidney disease or patients requiring or with a recent history of immunosuppressive therapy for kidney disease. FARXIGA is not expected to be effective in these populations.

2 DOSAGE AND ADMINISTRATION

2.1 Prior to Initiation of FARXIGA

- Assess renal function prior to initiation of FARXIGA therapy and then as clinically indicated [see Warnings and Precautions (5.2)].
- Assess volume status. In patients with volume depletion, correct this condition before initiating FARXIGA [see Warnings and Precautions (5.2) and Use in Specific Populations (8.5, 8.6)].

2.2 Recommended Dosage for Glycemic Control in Adults and Pediatric Patients Aged 10 Years and Older with Type 2 Diabetes Mellitus

In adults and pediatric patients aged 10 years and older with type 2 diabetes mellitus, the recommended starting dosage of FARXIGA is 5 mg orally once daily to improve glycemic control. For additional glycemic control, the dosage can be increased to 10 mg orally once daily.

For Adult and Pediatric Patients with Type 2 Diabetes Mellitus and Renal Impairment:

- The recommended dosage for FARXIGA in patients with an eGFR greater than or equal to 45 mL/min/1.73 m^2 is the same as the recommended dosage in patients with normal renal function.
- FARXIGA is not recommended for use to improve glycemic control in patients with type 2 diabetes mellitus with an eGFR less than 45 mL/min/1.73 m^2. FARXIGA is likely to be ineffective to improve glycemic control in this setting based upon its mechanism of action.

2.3 Recommended Dosage for Other Indications in Adults

The recommended dosage of FARXIGA is 10 mg orally once daily in adults for the following indications:

- To reduce the risk of sustained eGFR decline, end stage kidney disease (ESKD), cardiovascular (CV) death, and hospitalization for heart failure (hHF) in patients with chronic kidney disease at risk of progression.
- To reduce the risk of CV death, hHF, and urgent heart failure visit in patients with heart failure.
- To reduce the risk of hHF in patients with type 2 diabetes mellitus and either established CV disease or multiple CV risk factors.

For Adults with Renal Impairment Receiving FARXIGA for Indications Other than Glycemic Control:

- The recommended dosage of FARXIGA in patients with an eGFR greater than or equal to 25 mL/min/1.73 m^2 is the same as the recommended dosage in patients with normal renal function.
- Initiation with FARXIGA is not recommended in patients with an eGFR less than 25 mL/min/1.73 m^2.
- If the eGFR falls below 25 mL/min/1.73 m^2 while receiving treatment with FARXIGA, patients may continue FARXIGA 10 mg orally once daily to reduce the risk of eGFR decline, ESKD, CV death and hHF.

2.4 Temporary Interruption for Surgery

Withhold FARXIGA for at least 3 days, if possible, prior to major surgery or procedures associated with prolonged fasting. Resume FARXIGA when the patient is clinically stable and has resumed oral intake [see Warnings and Precautions (5.1) and Clinical Pharmacology (12.2)].

3 DOSAGE FORMS AND STRENGTHS

3 DOSAGE FORMS AND STRENGTHS

Tablets:

- 5 mg yellow, biconvex, round, film-coated tablets with “5” engraved on one side and “1427” engraved on the other side.
- 10 mg yellow, biconvex, diamond-shaped, film-coated tablets with “10” engraved on one side and “1428” engraved on the other side.

4 CONTRAINDICATIONS

FARXIGA is contraindicated in patients with a history of a serious hypersensitivity reaction to dapagliflozin or any of the excipients in FARXIGA. Serious hypersensitivity reactions, including anaphylaxis and angioedema have been reported with FARXIGA [see Adverse Reactions (6.1)].

5 WARNINGS AND PRECAUTIONS

5.1 Diabetic Ketoacidosis in Patients with Type 1 Diabetes Mellitus and Other Ketoacidosis

In patients with type 1 diabetes mellitus, FARXIGA significantly increases the risk of diabetic ketoacidosis, a life-threatening event, beyond the background rate. In placebo-controlled trials of patients with type 1 diabetes mellitus, the risk of ketoacidosis was markedly increased in patients who received sodium-glucose cotransporter 2 (SGLT2) inhibitors compared to patients who received placebo. FARXIGA is not indicated for glycemic control in patients with type 1 diabetes mellitus.

Type 2 diabetes mellitus and pancreatic disorders (e.g., history of pancreatitis or pancreatic surgery) are also risk factors for ketoacidosis. There have been postmarketing reports of fatal events of ketoacidosis in patients with type 2 diabetes mellitus using SGLT2 inhibitors, including FARXIGA.

Precipitating conditions for diabetic ketoacidosis or other ketoacidosis include under-insulinization due to insulin dose reduction or missed insulin doses, acute febrile illness, reduced caloric intake, ketogenic diet, surgery, volume depletion, and alcohol abuse.

Signs and symptoms are consistent with dehydration and severe metabolic acidosis and include nausea, vomiting, abdominal pain, generalized malaise, and shortness of breath. Blood glucose levels at presentation may be below those typically expected for diabetic ketoacidosis (e.g., less than 250 mg/dL). Ketoacidosis and glucosuria may persist longer than typically expected. Urinary glucose excretion persists for 3 days after discontinuing FARXIGA [see Clinical Pharmacology (12.2)]; however, there have been postmarketing reports of ketoacidosis and/or glucosuria lasting greater than 6 days and some up to 2 weeks after discontinuation of SGLT2 inhibitors.

Consider ketone monitoring in patients with type 1 diabetes mellitus and consider ketone monitoring in others at risk for ketoacidosis if indicated by the clinical situation. Assess for ketoacidosis regardless of presenting blood glucose levels in patients who present with signs and symptoms consistent with severe metabolic acidosis. If ketoacidosis is suspected, discontinue FARXIGA, promptly evaluate, and treat ketoacidosis, if confirmed. Monitor patients for resolution of ketoacidosis before restarting FARXIGA.

Withhold FARXIGA, if possible, in temporary clinical situations that could predispose patients to ketoacidosis. Resume FARXIGA when the patient is clinically stable and has resumed oral intake [see Dosage and Administration (2.3)].

Educate all patients on the signs and symptoms of ketoacidosis and instruct patients to discontinue FARXIGA and seek medical attention immediately if signs and symptoms occur.

5.2 Volume Depletion

FARXIGA can cause intravascular volume depletion which may sometimes manifest as symptomatic hypotension or acute transient changes in creatinine. There have been post-marketing reports of acute kidney injury, some requiring hospitalization and dialysis, in patients with type 2 diabetes mellitus receiving SGLT2 inhibitors, including FARXIGA. Patients with impaired renal function (eGFR less than 60 mL/min/1.73 m^2), elderly patients, or patients on loop diuretics may be at increased risk for volume depletion or hypotension. Before initiating FARXIGA in patients with one or more of these characteristics, assess volume status and renal function. Monitor for signs and symptoms of hypotension, and renal function after initiating therapy.

5.3 Urosepsis and Pyelonephritis

Serious urinary tract infections including urosepsis and pyelonephritis requiring hospitalization have been reported in patients receiving SGLT2 inhibitors, including FARXIGA. Treatment with SGLT2 inhibitors increases the risk for urinary tract infections. Evaluate patients for signs and symptoms of urinary tract infections and treat promptly, if indicated [see Adverse Reactions (6)].

5.4 Hypoglycemia with Concomitant Use with Insulin and Insulin Secretagogues

Insulin and insulin secretagogues (e.g., sulfonylureas) are known to cause hypoglycemia. FARXIGA may increase the risk of hypoglycemia when combined with insulin or an insulin secretagogue [see Adverse Reactions (6.1)]. Therefore, a lower dose of insulin or insulin secretagogue may be required to minimize the risk of hypoglycemia when these agents are used in combination with FARXIGA [see Drug Interactions (7)].

5.5 Necrotizing Fasciitis of the Perineum (Fournier’s Gangrene)

Reports of necrotizing fasciitis of the perineum (Fournier’s Gangrene), a rare but serious and life-threatening necrotizing infection requiring urgent surgical intervention, have been identified in postmarketing surveillance in patients with diabetes mellitus receiving SGLT2 inhibitors, including FARXIGA. Cases have been reported in both females and males. Serious outcomes have included hospitalization, multiple surgeries, and death.

Patients treated with FARXIGA presenting with pain or tenderness, erythema, or swelling in the genital or perineal area, along with fever or malaise, should be assessed for necrotizing fasciitis. If suspected, start treatment immediately with broad-spectrum antibiotics and, if necessary, surgical debridement. Discontinue FARXIGA, closely monitor blood glucose levels, and provide appropriate alternative therapy for glycemic control.

5.6 Genital Mycotic Infections

FARXIGA increases the risk of genital mycotic infections. Patients with a history of genital mycotic infections were more likely to develop genital mycotic infections [see Adverse Reactions (6.1)]. Monitor and treat appropriately.

6 ADVERSE REACTIONS

The following important adverse reactions are described below and elsewhere in the labeling:

- Diabetic Ketoacidosis in Patients with Type 1 Diabetes Mellitus and Other Ketoacidosis [see Warnings and Precautions (5.1)]
- Volume Depletion [see Warnings and Precautions (5.2)]
- Urosepsis and Pyelonephritis [see Warnings and Precautions (5.3)]
- Hypoglycemia with Concomitant Use with Insulin and Insulin Secretagogues [see Warnings and Precautions (5.4)]
- Necrotizing Fasciitis of the Perineum (Fournier’s Gangrene) [see Warnings and Precautions (5.5)]
- Genital Mycotic Infections [see Warnings and Precautions (5.6)]

6.1 Clinical Trials Experience

Because clinical trials are conducted under widely varying conditions, adverse reaction rates observed in the clinical trials of a drug cannot be directly compared to rates in the clinical trials of another drug and may not reflect the rates observed in clinical practice.

FARXIGA has been evaluated in clinical trials in adult and pediatric patients aged 10 years and older with type 2 diabetes mellitus, in adult patients with heart failure, and in adult patients with chronic kidney disease. The overall safety profile of FARXIGA was consistent across the studied indications. No new adverse reactions were identified in the DAPA-HF and DELIVER heart failure trials, or in the DAPA-CKD trial in patients with chronic kidney disease. Severe hypoglycemia and diabetic ketoacidosis (DKA) were observed only in patients with diabetes mellitus.

ClinicalTrials for Glycemic Control in Adult Patients with Type 2 Diabetes Mellitus

Pool of 12 Placebo-Controlled Adult Trials for FARXIGA 5 and 10 mg for Glycemic Control

The data in Table 1 is derived from 12 glycemic control placebo-controlled trials in adult patients with type 2 diabetes mellitus ranging from 12 to 24 weeks. In 4 trials FARXIGA was used as monotherapy, and in 8 trials FARXIGA was used as add-on to background antidiabetic therapy or as combination therapy with metformin [see Clinical Studies (14.1)].

These data reflect exposure of 2338 adult patients to FARXIGA with a mean exposure duration of 21 weeks. Patients received placebo (N=1393), FARXIGA 5 mg (N=1145), or FARXIGA 10 mg (N=1193) once daily. The mean age of the population was 55 years and 2% were older than 75 years of age. Fifty percent (50%) of the population were male; 81% were White, 14% were Asian, and 3% were Black or African American. At baseline, the population had diabetes for an average of 6 years, had a mean hemoglobin A1c (HbA1c) of 8.3%, and 21% had established microvascular complications of diabetes. Baseline renal function was normal or mildly impaired in 92% of patients and moderately impaired in 8% of patients (mean eGFR 86 mL/min/1.73 m^2).

Table 1 shows common adverse reactions in adults associated with the use of FARXIGA. These adverse reactions were not present at baseline, occurred more commonly on FARXIGA than on placebo, and occurred in at least 2% of patients treated with either FARXIGA 5 mg or FARXIGA 10 mg.

Table 1: Adverse Reactions in Placebo-Controlled Trials of Glycemic Control Reported in ≥2% of Adults Treated with FARXIGA
Adverse Reaction | % of Patients
 | Pool of 12 Placebo-Controlled Trials
 | Placebo N=1393 | FARXIGA 5 mg N=1145 | FARXIGA 10 mg N=1193
Female genital mycotic infections [Genital mycotic infections include the following adverse reactions, listed in order of frequency reported for females: vulvovaginal mycotic infection, vaginal infection, vulvovaginal candidiasis, vulvovaginitis, genital infection, genital candidiasis, fungal genital infection, vulvitis, genitourinary tract infection, vulval abscess, and vaginitis bacterial. (N for females: Placebo=677, FARXIGA 5 mg=581, FARXIGA 10 mg=598).] | 1.5 | 8.4 | 6.9
Nasopharyngitis | 6.2 | 6.6 | 6.3
Urinary tract infections [Urinary tract infections include the following adverse reactions, listed in order of frequency reported: urinary tract infection, cystitis, Escherichia urinary tract infection, genitourinary tract infection, pyelonephritis, trigonitis, urethritis, kidney infection, and prostatitis.] | 3.7 | 5.7 | 4.3
Back pain | 3.2 | 3.1 | 4.2
Increased urination [Increased urination includes the following adverse reactions, listed in order of frequency reported: pollakiuria, polyuria, and urine output increased.] | 1.7 | 2.9 | 3.8
Male genital mycotic infections [Genital mycotic infections include the following adverse reactions, listed in order of frequency reported for males: balanitis, fungal genital infection, balanitis candida, genital candidiasis, genital infection male, penile infection, balanoposthitis, balanoposthitis infective, genital infection, and posthitis. (N for males: Placebo=716, FARXIGA 5 mg=564, FARXIGA 10 mg=595).] | 0.3 | 2.8 | 2.7
Nausea | 2.4 | 2.8 | 2.5
Influenza | 2.3 | 2.7 | 2.3
Dyslipidemia | 1.5 | 2.1 | 2.5
Constipation | 1.5 | 2.2 | 1.9
Discomfort with urination | 0.7 | 1.6 | 2.1
Pain in extremity | 1.4 | 2.0 | 1.7

Pool of 13 Placebo-Controlled Adult Trials for FARXIGA 10 mg for Glycemic Control

FARXIGA 10 mg was also evaluated in a larger glycemic control placebo-controlled trial pool in adult patients with type 2 diabetes mellitus. This pool combined 13 placebo-controlled trials, including 3 monotherapy trials, 9 add-on to background antidiabetic therapy trials, and an initial combination with metformin trial. Across these 13 trials, 2360 patients were treated once daily with FARXIGA 10 mg for a mean duration of exposure of 22 weeks. The mean age of the population was 59 years and 4% were older than 75 years. Fifty-eight percent (58%) of the population were male; 84% were White, 9% were Asian, and 3% were Black or African American. At baseline, the population had diabetes for an average of 9 years, had a mean HbA1c of 8.2%, and 30% had established microvascular disease. Baseline renal function was normal or mildly impaired in 88% of patients and moderately impaired in 11% of patients (mean eGFR 82 mL/min/1.73 m^2).

Other Adverse Reactions in Adult Patients with Type 2 Diabetes Mellitus

Volume Depletion

FARXIGA causes an osmotic diuresis, which may lead to a reduction in intravascular volume. Adverse reactions related to volume depletion (including reports of dehydration, hypovolemia, orthostatic hypotension, or hypotension) in adult patients with type 2 diabetes mellitus for the 12-trial and 13-trial, short-term, placebo-controlled pools and for the DECLARE trial are shown in Table 2 [see Warnings and Precautions (5.2)].

Table 2: Adverse Reactions Related to Volume Depletion [Volume depletion includes reports of dehydration, hypovolemia, orthostatic hypotension, or hypotension.] in Clinical Trials in Adults with Type 2 Diabetes Mellitus with FARXIGA
 | Pool of 12 Placebo-Controlled Trials |  |  | Pool of 13 Placebo-Controlled Trials |  | DECLARE Trial
 | Placebo | FARXIGA 5 mg | FARXIGA 10 mg | Placebo | FARXIGA 10 mg | Placebo | FARXIGA 10 mg
Overall population N (%) | N=1393 5 (0.4%) | N=1145 7 (0.6%) | N=1193 9 (0.8%) | N=2295 17 (0.7%) | N=2360 27 (1.1%) | N=8569 207 (2.4%) | N=8574 213 (2.5%)
Patient Subgroup n (%)
Patients on loop diuretics | n=55 1 (1.8%) | n=40 0 | n=31 3 (9.7%) | n=267 4 (1.5%) | n=236 6 (2.5%) | n=934 57 (6.1%) | n=866 57 (6.6%)
Patients with moderate renal impairment with eGFR ≥30 and <60 mL/min/1.73 m^2 | n=107 2 (1.9%) | n=107 1 (0.9%) | n=89 1 (1.1%) | n=268 4 (1.5%) | n=265 5 (1.9%) | n=658 30 (4.6%) | n=604 35 (5.8%)
Patients ≥65 years of age | n=276 1 (0.4%) | n=216 1 (0.5%) | n=204 3 (1.5%) | n=711 6 (0.8%) | n=665 11 (1.7%) | n=3950 121 (3.1%) | n=3948 117 (3.0%)

Hypoglycemia

The frequency of hypoglycemia by trial in adult patients with type 2 diabetes mellitus [see Clinical Studies (14.1)] is shown in Table 3. Hypoglycemia was more frequent when FARXIGA was added to sulfonylurea or insulin [see Warnings and Precautions (5.4)].

Table 3: Incidence of Severe Hypoglycemia [Severe episodes of hypoglycemia were defined as episodes of severe impairment in consciousness or behavior, requiring external (third party) assistance, and with prompt recovery after intervention regardless of glucose level.] and Hypoglycemia with Glucose < 54 mg/dL [Episodes of hypoglycemia with glucose <54 mg/dL (3 mmol/L) were defined as reported episodes of hypoglycemia meeting the glucose criteria that did not also qualify as a severe episode.] in Controlled Glycemic Control Clinical Trials in Adults with Type 2 Diabetes Mellitus
 | Placebo/Active Control | FARXIGA 5 mg | FARXIGA 10 mg
Monotherapy (24 weeks) | N=75 | N=64 | N=70
Severe [n (%)] | 0 | 0 | 0
Glucose <54 mg/dL [n (%)] | 0 | 0 | 0
Add-on to Metformin (24 weeks) | N=137 | N=137 | N=135
Severe [n (%)] | 0 | 0 | 0
Glucose <54 mg/dL [n (%)] | 0 | 0 | 0
Add-on to Glimepiride (24 weeks) | N=146 | N=145 | N=151
Severe [n (%)] | 0 | 0 | 0
Glucose <54 mg/dL [n (%)] | 1 (0.7) | 3 (2.1) | 5 (3.3)
Add-on to Metformin and a Sulfonylurea (24 Weeks) | N=109 | - | N=109
Severe [n (%)] | 0 | - | 0
Glucose <54 mg/dL [n (%)] | 3 (2.8) | - | 7 (6.4)
Add-on to Pioglitazone (24 weeks) | N=139 | N=141 | N=140
Severe [n (%)] | 0 | 0 | 0
Glucose <54 mg/dL [n (%)] | 0 | 1 (0.7) | 0
Add-on to DPP4 inhibitor (24 weeks) | N=226 | – | N=225
Severe [n (%)] | 0 | – | 1 (0.4)
Glucose <54 mg/dL [n (%)] | 1 (0.4) | – | 1 (0.4)
Add-on to Insulin with or without other OADs [OAD = oral antidiabetic therapy.] (24 weeks) | N=197 | N=212 | N=196
Severe [n (%)] | 1 (0.5) | 2 (0.9) | 2 (1.0)
Glucose <54 mg/dL [n (%)] | 43 (21.8) | 55 (25.9) | 45 (23.0)

In the DECLARE trial [see Clinical Studies (14.3)], severe events of hypoglycemia were reported in 58 (0.7%) out of 8574 adult patients treated with FARXIGA and 83 (1.0%) out of 8569 adult patients treated with placebo.

Genital Mycotic Infections

In the glycemic control trials in adults, genital mycotic infections were more frequent with FARXIGA treatment. Genital mycotic infections were reported in 0.9% of patients on placebo, 5.7% on FARXIGA 5 mg, and 4.8% on FARXIGA 10 mg, in the 12-trial placebo-controlled pool. Discontinuation from trial due to genital infection occurred in 0% of placebo-treated patients and 0.2% of patients treated with FARXIGA 10 mg. Infections were more frequently reported in females than in males (see Table 1). The most frequently reported genital mycotic infections were vulvovaginal mycotic infections in females and balanitis in males. Patients with a history of genital mycotic infections were more likely to have a genital mycotic infection during the trial than those with no prior history (10.0%, 23.1%, and 25.0% versus 0.8%, 5.9%, and 5.0% on placebo, FARXIGA 5 mg, and FARXIGA 10 mg, respectively). In the DECLARE trial [see Clinical Studies (14.3)], serious genital mycotic infections were reported in <0.1% of patients treated with FARXIGA and <0.1% of patients treated with placebo. Genital mycotic infections that caused trial drug discontinuation were reported in 0.9% of patients treated with FARXIGA and <0.1% of patients treated with placebo.

Hypersensitivity Reactions

Hypersensitivity reactions (e.g., angioedema, urticaria, hypersensitivity) were reported with FARXIGA treatment. In glycemic control trials in adults, serious anaphylactic reactions and severe cutaneous adverse reactions and angioedema were reported in 0.2% of comparator-treated patients and 0.3% of FARXIGA-treated patients. If hypersensitivity reactions occur, discontinue use of FARXIGA; treat per standard of care and monitor until signs and symptoms resolve.

Ketoacidosis in Patients with Diabetes Mellitus

In the DECLARE trial [see Clinical Studies (14.3)], events of diabetic ketoacidosis (DKA) were reported in 27 out of 8574 adult patients in the FARXIGA-treated group and 12 out of 8569 adult patients in the placebo group. The events were evenly distributed over the trial period.

Laboratory Tests in Adult Patients with Type 2 Diabetes Mellitus

Increases in Serum Creatinine and Decreases in eGFR

Initiation of SGLT2 inhibitors, including FARXIGA causes a small increase in serum creatinine and decrease in eGFR. These changes in serum creatinine and eGFR generally occur within two weeks of starting therapy and then stabilize regardless of baseline kidney function. Changes that do not fit this pattern should prompt further evaluation to exclude the possibility of acute kidney injury [see Warnings and Precautions (5.2)]. In two trials that included adult patients with type 2 diabetes mellitus with moderate renal impairment, the acute effect on eGFR reversed after treatment discontinuation, suggesting acute hemodynamic changes may play a role in the renal function changes observed with FARXIGA.

Increase in Hematocrit

In the pool of 13 placebo-controlled trials of glycemic control, increases from baseline in mean hematocrit values were observed in FARXIGA-treated adult patients starting at Week 1 and continuing up to Week 16, when the maximum mean difference from baseline was observed. At Week 24, the mean changes from baseline in hematocrit were -0.33% in the placebo group and 2.30% in the FARXIGA 10 mg group. By Week 24, hematocrit values >55% were reported in 0.4% of placebo-treated patients and 1.3% of FARXIGA 10 mg-treated patients.

Increase in Low-Density Lipoprotein Cholesterol

In the pool of 13 placebo-controlled trials of glycemic control, changes from baseline in mean lipid values were reported in FARXIGA-treated adult patients compared to placebo-treated patients. Mean percent changes from baseline at Week 24 were 0.0% versus 2.5% for total cholesterol, and -1.0% versus 2.9% for LDL cholesterol in the placebo and FARXIGA 10 mg groups, respectively. In the DECLARE trial [see Clinical Studies (14.3)], mean changes from baseline after 4 years were 0.4 mg/dL versus -4.1 mg/dL for total cholesterol, and -2.5 mg/dL versus -4.4 mg/dL for LDL cholesterol, in FARXIGA-treated and the placebo groups, respectively.

Decrease in Serum Bicarbonate

In a trial of concomitant therapy of FARXIGA 10 mg with exenatide extended-release (on a background of metformin) in adults, four patients (1.7%) on concomitant therapy had a serum bicarbonate value of less than or equal to 13 mEq/L compared to one each (0.4%) in the FARXIGA and exenatide-extended release treatment groups [see Warnings and Precautions (5.1)].

Clinical Trial in Pediatric Patients with Type 2 Diabetes Mellitus

The FARXIGA safety profile observed in a 26-week placebo-controlled clinical trial with a 26-week extension in 157 pediatric patients aged 10 years and older with type 2 diabetes mellitus was similar to that observed in adults [see Clinical Studies (14.2)].

6.2 Postmarketing Experience

Additional adverse reactions have been identified during post-approval use of FARXIGA in patients with diabetes mellitus. Because these reactions are reported voluntarily from a population of uncertain size, it is generally not possible to reliably estimate their frequency or establish a causal relationship to drug exposure.

Infections: Necrotizing fasciitis of the perineum (Fournier’s Gangrene), urosepsis and pyelonephritis

Metabolism and Nutrition Disorders: Ketoacidosis

Renal and Urinary Disorders: Acute kidney injury

Skin and Subcutaneous Tissue Disorders: Rash

7 DRUG INTERACTIONS

Table 4: Clinically Relevant Interactions with FARXIGA
Insulin or Insulin Secretagogues
Clinical Impact | The risk of hypoglycemia may be increased when FARXIGA is used concomitantly with insulin or insulin secretagogues (e.g., sulfonylurea) [see Warnings and Precautions (5.4)].
Intervention | Concomitant use may require lower doses of insulin or the insulin secretagogue to reduce the risk of hypoglycemia.
Lithium
Clinical Impact | Concomitant use of an SGLT2 inhibitor with lithium may decrease serum lithium concentrations.
Intervention | Monitor serum lithium concentration more frequently during FARXIGA initiation and dosage changes.
Positive Urine Glucose Test
Clinical Impact | SGLT2 inhibitors increase urinary glucose excretion and will lead to positive urine glucose tests.
Intervention | Monitoring glycemic control with urine glucose tests is not recommended in patients taking SGLT2 inhibitors. Use alternative methods to monitor glycemic control.
Interference with 1,5-anhydroglucitol (1,5-AG) Assay
Clinical Impact | Measurements of 1,5-AG are unreliable in assessing glycemic control in patients taking SGLT2 inhibitors.
Intervention | Monitoring glycemic control with 1,5-AG assay is not recommended. Use alternative methods to monitor glycemic control.

8 USE IN SPECIFIC POPULATIONS

8.1 Pregnancy

Risk Summary

Based on animal data showing adverse renal effects, FARXIGA is not recommended during the second and third trimesters of pregnancy.

Limited data with FARXIGA in pregnant women are not sufficient to determine drug-associated risk for major birth defects or miscarriage. There are risks to the mother and fetus associated with poorly controlled diabetes and untreated heart failure in pregnancy (see Clinical Considerations).

In animal studies, adverse renal pelvic and tubule dilatations, that were not fully reversible, were observed in rats when dapagliflozin was administered during a period of renal development corresponding to the late second and third trimesters of human pregnancy, at all doses tested; the lowest of which provided an exposure 15-times the 10 mg clinical dose (see Data).

The estimated background risk of major birth defects is 6 to 10% in women with pre-gestational diabetes with a HbA1c greater than 7% and has been reported to be as high as 20 to 25% in women with HbA1c greater than 10%. The estimated background risk of miscarriage for the indicated population is unknown. In the U.S. general population, the estimated background risk of major birth defects and miscarriage in clinically recognized pregnancies is 2 to 4% and 15 to 20%, respectively.

Clinical Considerations

Disease-associated maternal and/or embryofetal risk

Poorly controlled diabetes in pregnancy increases the maternal risk for diabetic ketoacidosis, preeclampsia, spontaneous abortions, preterm delivery and delivery complications. Poorly controlled diabetes increases the fetal risk for major birth defects, stillbirth, and macrosomia related morbidity.

Data

Animal Data

Dapagliflozin dosed directly to juvenile rats from postnatal day (PND) 21 until PND 90 at doses of 1, 15, or 75 mg/kg/day, increased kidney weights and increased the incidence of renal pelvic and tubular dilatations at all dose levels. Exposure at the lowest dose tested was 15-times the 10 mg clinical dose (based on AUC). The renal pelvic and tubular dilatations observed in juvenile animals did not fully reverse within a 1-month recovery period.

In a prenatal and postnatal development study, dapagliflozin was administered to maternal rats from gestation day 6 through lactation day 21 at doses of 1, 15, or 75 mg/kg/day, and pups were indirectly exposed in utero and throughout lactation. Increased incidence or severity of renal pelvic dilatation was observed in 21-day-old pups offspring of treated dams at 75 mg/kg/day (maternal and pup dapagliflozin exposures were 1415-times and 137-times, respectively, the human values at the 10 mg clinical dose, based on AUC). Dose-related reductions in pup body weights were observed at greater or equal to 29-times the 10 mg clinical dose (based on AUC). No adverse effects on developmental endpoints were noted at 1 mg/kg/day (19-times the 10 mg clinical dose, based on AUC). These outcomes occurred with drug exposure during periods of renal development in rats that corresponds to the late second and third trimester of human development.

In embryofetal development studies in rats and rabbits, dapagliflozin was administered throughout organogenesis, corresponding to the first trimester of human pregnancy. In rats, dapagliflozin was neither embryolethal nor teratogenic at doses up to 75 mg/kg/day (1441-times the 10 mg clinical dose, based on AUC). Dose-related effects on the rat fetus (structural abnormalities and reduced body weight) occurred only at higher dosages, equal to or greater than 150 mg/kg (more than 2344-times the 10 mg clinical dose, based on AUC), which were associated with maternal toxicity. No developmental toxicities were observed in rabbits at doses up to 180 mg/kg/day (1191-times the 10 mg clinical dose, based on AUC).

8.2 Lactation

Risk Summary

There is no information regarding the presence of dapagliflozin in human milk, the effects on the breastfed infant, or the effects on milk production. Dapagliflozin is present in the milk of lactating rats (see Data). However, due to species-specific differences in lactation physiology, the clinical relevance of these data is not clear. Since human kidney maturation occurs in utero and during the first 2 years of life when lactational exposure may occur, there may be risk to the developing human kidney.

Because of the potential for serious adverse reactions in breastfed infants, advise women that use of FARXIGA is not recommended while breastfeeding.

Data

Dapagliflozin was present in rat milk at a milk/plasma ratio of 0.49, indicating that dapagliflozin and its metabolites are transferred into milk at a concentration that is approximately 50% of that in maternal plasma. Juvenile rats directly exposed to dapagliflozin showed risk to the developing kidney (renal pelvic and tubular dilatations) during maturation.

8.4 Pediatric Use

The safety and effectiveness of FARXIGA as an adjunct to diet and exercise to improve glycemic control in type 2 diabetes mellitus have been established in pediatric patients aged 10 years and older. Use of FARXIGA for this indication is supported by a 26-week placebo-controlled trial with a 26-week extension in 157 pediatric patients aged 10 to 17 years with type 2 diabetes mellitus, pediatric pharmacokinetic data, and trials in adults with type 2 diabetes mellitus [see Clinical Pharmacology (12.3) and Clinical Studies (14.1, 14.2)]. The safety profile observed in the placebo-controlled trial in pediatric patients with type 2 diabetes mellitus was similar to that observed in adults [see Adverse Reactions (6.1)].

The safety and effectiveness of FARXIGA for glycemic control in type 2 diabetes mellitus have not been established in pediatric patients less than 10 years of age.

The safety and effectiveness of FARXIGA have not been established in pediatric patients to reduce the risk of [see Indications and Usage (1)].

- sustained eGFR decline, end stage kidney disease, cardiovascular death, and hospitalization for heart failure in patients with chronic kidney disease at risk of progression.
- cardiovascular death, hospitalization for heart failure, and urgent heart failure visit in patients with heart failure.
- hospitalization for heart failure in patients with type 2 diabetes mellitus and either established cardiovascular disease or multiple cardiovascular risk factors.

8.5 Geriatric Use

No FARXIGA dosage change is recommended based on age.

A total of 1424 (24%) of the 5936 FARXIGA-treated patients were 65 years and older and 207 (3.5%) patients were 75 years and older in a pool of 21 double-blind, controlled, clinical trials assessing the efficacy of FARXIGA in improving glycemic control in type 2 diabetes mellitus. After controlling for level of renal function (eGFR), efficacy was similar for patients under age 65 years and those 65 years and older. In patients ≥65 years of age, a higher proportion of patients treated with FARXIGA for glycemic control had adverse reactions of hypotension [see Warnings and Precautions (5.2) and Adverse Reactions (6.1)].

In the DAPA-CKD, DAPA-HF and DELIVER trials, safety and efficacy were similar for patients aged 65 years and younger and those older than 65. In the DAPA-HF study, 2714 (57%) out of 4744 patients with HFrEF were older than 65 years. In the DELIVER study, 4759 (76%) out of 6263 patients with heart failure (LVEF >40%) were older than 65 years. In the DAPA-CKD study, 1818 (42%) out of 4304 patients with CKD were older than 65 years.

8.6 Renal Impairment

FARXIGA was evaluated in 4304 adult patients with chronic kidney disease (eGFR 25 to 75 mL/min/1.73 m^2) in the DAPA-CKD trial. FARXIGA was also evaluated in 1926 adult patients with an eGFR of 30 to 60 mL/min/1.73 m^2 in the DAPA-HF trial. The safety profile of FARXIGA across eGFR subgroups in these studies was consistent with the known safety profile [see Adverse Reactions (6.1) and Clinical Studies (14.4, 14.5)].

FARXIGA was evaluated in two glycemic control adult trials that included patients with type 2 diabetes mellitus with moderate renal impairment (an eGFR of 45 to less than 60 mL/min/1.73 m^2 [see Clinical Studies (14.1)], and an eGFR of 30 to less than 60 mL/min/1.73 m^2, respectively). Patients with diabetes and renal impairment using FARXIGA may be more likely to experience hypotension and may be at higher risk for acute kidney injury secondary to volume depletion. In the trial of adult patients with an eGFR 30 to less than 60 mL/min/1.73 m^2, 13 patients receiving FARXIGA experienced bone fractures compared to none receiving placebo. Use of FARXIGA for glycemic control in patients without established CV disease or CV risk factors is not recommended when eGFR is less than 45 mL/min/1.73 m^2 [see Dosage and Administration (2.1)].

Efficacy and safety trials with FARXIGA did not enroll patients with an eGFR less than 25 mL/min/1.73 m^2 or on dialysis. Once enrolled in the DAPA-CKD and DELIVER trials, adult patients were not required to discontinue therapy if eGFR fell below 25 mL/min/1.73 m^2 or if dialysis was initiated. Once enrolled in the DAPA-HF trial, adult patients were not required to discontinue therapy if eGFR fell below 30 mL/min/1.73 m^2 or if dialysis was initiated [see Dosage and Administration (2.3) and Clinical Studies (14.4,14.5)].

8.7 Hepatic Impairment

No dose adjustment is recommended for patients with mild, moderate, or severe hepatic impairment. However, the benefit-risk for the use of dapagliflozin in patients with severe hepatic impairment should be individually assessed since the safety and efficacy of dapagliflozin have not been specifically studied in this population [see Clinical Pharmacology (12.3)].

10 OVERDOSAGE

There were no reports of overdose during the clinical development program for FARXIGA.

In the event of an overdose, consider contacting the Poison Help line (1-800-222-1222) or a medical toxicologist for additional overdosage management recommendations. It is also reasonable to employ supportive measures as dictated by the patient’s clinical status. The removal of dapagliflozin by hemodialysis has not been studied.

11 DESCRIPTION

Dapagliflozin, an inhibitor of SGLT2, is described chemically as D-glucitol, 1,5-anhydro-1-C-[4-chloro-3-[(4-ethoxyphenyl)methyl]phenyl]-, (1S)-, compounded with (2S)-1,2-propanediol, hydrate (1:1:1). The empirical formula is C21H25ClO6•C3H8O2•H2O and the molecular weight is 502.98. The structural formula is:

FARXIGA is available as a film-coated tablet for oral administration containing the equivalent of 5 mg dapagliflozin as dapagliflozin propanediol or the equivalent of 10 mg dapagliflozin as dapagliflozin propanediol, and the following inactive ingredients: anhydrous lactose, crospovidone, magnesium stearate, microcrystalline cellulose, and silicon dioxide. In addition, the film coating contains the following inactive ingredients: polyethylene glycol, polyvinyl alcohol, talc, titanium dioxide, and yellow iron oxide.

12 CLINICAL PHARMACOLOGY

12.1 Mechanism of Action

Sodium-glucose cotransporter 2 (SGLT2), expressed in the proximal renal tubules, is responsible for the majority of the reabsorption of filtered glucose from the tubular lumen. Dapagliflozin is an inhibitor of SGLT2. By inhibiting SGLT2, dapagliflozin reduces reabsorption of filtered glucose and thereby promotes urinary glucose excretion.

Dapagliflozin also reduces sodium reabsorption and increases the delivery of sodium to the distal tubule. This may influence several physiological functions including, but not restricted to, lowering both pre- and afterload of the heart and downregulation of sympathetic activity, and decreased intraglomerular pressure which is believed to be mediated by increased tubuloglomerular feedback.

12.2 Pharmacodynamics

General

Increases in the amount of glucose excreted in the urine were observed in healthy subjects and in patients with type 2 diabetes mellitus following the administration of dapagliflozin (see Figure 1). Dapagliflozin doses of 5 or 10 mg per day in patients with type 2 diabetes mellitus for 12 weeks resulted in excretion of approximately 70 grams of glucose in the urine per day at Week 12. A near maximum glucose excretion was observed at the dapagliflozin daily dosage of 20 mg. This urinary glucose excretion with dapagliflozin also results in increases in urinary volume [see Adverse Reactions (6.1)]. After discontinuation of dapagliflozin, on average, the elevation in urinary glucose excretion approaches baseline by about 3 days for the 10 mg dosage.

Figure 1: Scatter Plot and Fitted Line of Change from Baseline in 24-Hour Urinary Glucose Amount versus Dapagliflozin Dose in Healthy Subjects and Subjects with Type 2 Diabetes Mellitus (T2DM) (Semi-Log Plot)

Cardiac Electrophysiology

Dapagliflozin was not associated with clinically meaningful prolongation of QTc interval at daily doses up to 150 mg (15-times the recommended maximum dose) in a study of healthy subjects. In addition, no clinically meaningful effect on QTc interval was observed following single doses of up to 500 mg (50-times the recommended maximum dose) of dapagliflozin in healthy subjects.

12.3 Pharmacokinetics

Absorption

Following oral administration of dapagliflozin, the maximum plasma concentration (Cmax) is usually attained within 2 hours under fasting state. The Cmax and AUC values increase dose proportionally with increase in dapagliflozin dose in the therapeutic dose range. The absolute oral bioavailability of dapagliflozin following the administration of a 10 mg dose is 78%. Administration of dapagliflozin with a high-fat meal decreases its Cmax by up to 50% and prolongs Tmax by approximately 1 hour but does not alter AUC as compared with the fasted state. These changes are not considered to be clinically meaningful and dapagliflozin can be administered with or without food

Distribution

Dapagliflozin is approximately 91% protein bound. Protein binding is not altered in patients with renal or hepatic impairment.

Metabolism

The metabolism of dapagliflozin is primarily mediated by UGT1A9; CYP-mediated metabolism is a minor clearance pathway in humans. Dapagliflozin is extensively metabolized, primarily to yield dapagliflozin 3-O-glucuronide, which is an inactive metabolite. Dapagliflozin 3-O-glucuronide accounted for 61% of a 50 mg [^14C]-dapagliflozin dose and is the predominant drug-related component in human plasma.

Elimination

Dapagliflozin and related metabolites are primarily eliminated via the renal pathway. Following a single 50 mg dose of [^14C]-dapagliflozin, 75% and 21% total radioactivity is excreted in urine and feces, respectively. In urine, less than 2% of the dose is excreted as parent drug. In feces, approximately 15% of the dose is excreted as parent drug. The mean plasma terminal half-life (t½) for dapagliflozin is approximately 12.9 hours following a single oral dose of FARXIGA 10 mg.

Specific Populations

Pediatric Patients

The pharmacokinetics and pharmacodynamics (glucosuria) of dapagliflozin in pediatric patients aged 10 to 17 years with type 2 diabetes mellitus were similar to those observed in adult patients with same renal function.

Effects of Age, Gender, Race, and Body Weight on Pharmacokinetics

Based on a population pharmacokinetic analysis, age, gender, race, and body weight do not have a clinically meaningful effect on the pharmacokinetics of dapagliflozin and thus, no dose adjustment is recommended.

Patients with Renal Impairment

At steady state (20 mg once daily dapagliflozin for 7 days), adult patients with type 2 diabetes with mild, moderate, or severe renal impairment (as determined by eGFR) had geometric mean systemic exposures of dapagliflozin that were 45%, 100%, and 200% higher, respectively, as compared to patients with type 2 diabetes mellitus with normal renal function. There was no meaningful difference in exposure between patients with chronic kidney disease with and without type 2 diabetes. Higher systemic exposure of dapagliflozin in patients with type 2 diabetes mellitus with renal impairment did not result in a correspondingly higher 24-hour urinary glucose excretion. The steady-state 24-hour urinary glucose excretion in patients with type 2 diabetes mellitus and mild, moderate, and severe renal impairment was 42%, 80%, and 90% lower, respectively, than in patients with type 2 diabetes mellitus with normal renal function.

The impact of hemodialysis on dapagliflozin exposure is not known [see Warnings and Precautions (5.2), Use in Specific Populations (8.6), and Clinical Studies (14)]

Patients with Hepatic Impairment

In adult subjects with mild and moderate hepatic impairment (Child-Pugh classes A and B), mean Cmax and AUC of dapagliflozin were up to 12% and 36% higher, respectively, as compared to healthy matched control subjects following single-dose administration of 10 mg dapagliflozin. These differences were not considered to be clinically meaningful. In adult patients with severe hepatic impairment (Child-Pugh class C), mean Cmax and AUC of dapagliflozin were up to 40% and 67% higher, respectively, as compared to healthy matched controls [see Use in Specific Populations (8.7)].

Drug Interactions

In Vitro Assessment of Drug Interactions

In in vitro studies, dapagliflozin and dapagliflozin 3-O-glucuronide neither inhibited CYP 1A2, 2C9, 2C19, 2D6, or 3A4, nor induced CYP 1A2, 2B6, or 3A4. Dapagliflozin is a weak substrate of the P-glycoprotein (P-gp) active transporter, and dapagliflozin 3-O-glucuronide is a substrate for the OAT3 active transporter. Dapagliflozin or dapagliflozin 3-O-glucuronide did not meaningfully inhibit P-gp, OCT2, OAT1, or OAT3 active transporters. Overall, dapagliflozin is unlikely to affect the pharmacokinetics of concurrently administered medications that are P-gp, OCT2, OAT1, or OAT3 substrates.

Effects of Other Drugs on Dapagliflozin

Table 5 shows the effect of coadministered drugs on the pharmacokinetics of dapagliflozin in adults. No dose adjustments are recommended for dapagliflozin.

Table 5: Effects of Coadministered Drugs on Dapagliflozin Systemic Exposure
Coadministered Drug (Dose Regimen) [Single dose unless otherwise noted.] | Dapagliflozin (Dose Regimen) | Effect on Dapagliflozin Exposure (% Change [90% CI])
Coadministered Drug (Dose Regimen) [Single dose unless otherwise noted.] | Dapagliflozin (Dose Regimen) | Cmax | AUC [AUC = AUC(INF) for drugs given as single dose and AUC = AUC(TAU) for drugs given in multiple doses.]
No dosing adjustments required for the following:
Oral Antidiabetic Agents
Metformin (1000 mg) | 20 mg | ↔ | ↔
Pioglitazone (45 mg) | 50 mg | ↔ | ↔
Sitagliptin (100 mg) | 20 mg | ↔ | ↔
Glimepiride (4 mg) | 20 mg | ↔ | ↔
Voglibose (0.2 mg three times daily) | 10 mg | ↔ | ↔
Other Medications
Hydrochlorothiazide (25 mg) | 50 mg | ↔ | ↔
Bumetanide (1 mg) | 10 mg once daily for 7 days | ↔ | ↔
Valsartan (320 mg) | 20 mg | ↓12% [↓3%, ↓20%] | ↔
Simvastatin (40 mg) | 20 mg | ↔ | ↔
Anti-infective Agent
Rifampin (600 mg once daily for 6 days) | 10 mg | ↓7% [↓22%, ↑11%] | ↓22% [↓27%, ↓17%]
Nonsteroidal Anti-inflammatory Agent
Mefenamic Acid (loading dose of 500 mg followed by 14 doses of 250 mg every 6 hours) | 10 mg | ↑13% [↑3%, ↑24%] | ↑51% [↑44%, ↑58%]
↔ = no change (geometric mean ratio of test: reference within 0.80 to 1.25); ↓ or ↑ = parameter was lower or higher, respectively, with coadministration compared to dapagliflozin administered alone (geometric mean ratio of test: reference was lower than 0.80 or higher than 1.25).

Effects of Dapagliflozin on Other Drugs

Table 6 shows the effect of dapagliflozin on other coadministered drugs in adults. Dapagliflozin did not meaningfully affect the pharmacokinetics of the coadministered drugs.

Table 6: Effects of Dapagliflozin on the Systemic Exposures of Coadministered Drugs
Coadministered Drug (Dose Regimen) [Single dose unless otherwise noted.] | Dapagliflozin (Dose Regimen) | Effect on Coadministered Drug Exposure (% Change [90% CI])
Coadministered Drug (Dose Regimen) [Single dose unless otherwise noted.] | Dapagliflozin (Dose Regimen) | Cmax | AUC [AUC = AUC(INF) for drugs given as single dose and AUC = AUC(TAU) for drugs given in multiple doses.]
No dosing adjustments required for the following:
Oral Antidiabetic Agents
Metformin (1000 mg) | 20 mg | ↔ | ↔
Pioglitazone (45 mg) | 50 mg | ↓7% [↓25%, ↑15%] | ↔
Sitagliptin (100 mg) | 20 mg | ↔ | ↔
Glimepiride (4 mg) | 20 mg | ↔ | ↑13% [0%, ↑29%]
Other Medications
Hydrochlorothiazide (25 mg) | 50 mg | ↔ | ↔
Bumetanide (1 mg) | 10 mg once daily for 7 days | ↑13% [↓2%, ↑31%] | ↑13% [↓1%, ↑30%]
Valsartan (320 mg) | 20 mg | ↓6% [↓24%, ↑16%] | ↑5% [↓15%, ↑29%]
Simvastatin (40 mg) | 20 mg | ↔ | ↑19%
Digoxin (0.25 mg) | 20 mg loading dose then 10 mg once daily for 7 days | ↔ | ↔
Warfarin (25 mg) | 20 mg loading dose then 10 mg once daily for 7 days | ↔ | ↔
↔ = no change (geometric mean ratio of test: reference within 0.80 to 1.25); ↓ or ↑ = parameter was lower or higher, respectively, with coadministration compared to the other medicine administered alone (geometric mean ratio of test: reference was lower than 0.80 or higher than 1.25).

13 NONCLINICAL TOXICOLOGY

13.1 Carcinogenesis, Mutagenesis, Impairment of Fertility

Dapagliflozin did not induce tumors in either mice or rats at any of the doses evaluated in 2-year carcinogenicity studies. Oral doses in mice consisted of 5, 15, and 40 mg/kg/day in males and 2, 10, and 20 mg/kg/day in females, and oral doses in rats were 0.5, 2, and 10 mg/kg/day for both males and females. The highest doses evaluated in mice were approximately 72‑times (males) and 105‑times (females) the clinical dose of 10 mg per day, based on AUC exposure. In rats, the highest dose was approximately 131‑times (males) and 186‑times (females) the clinical dose of 10 mg per day, based on AUC exposure.

Dapagliflozin was negative in the Ames mutagenicity assay and was positive in a series of in vitro clastogenicity assays in the presence of S9 activation and at concentrations greater than or equal to 100 µg/mL. Dapagliflozin was negative for clastogenicity in a series of in vivo studies evaluating micronuclei or DNA repair in rats at exposure multiples greater than 2100‑times the clinical dose.

There was no carcinogenicity or mutagenicity signal in animal studies, suggesting that dapagliflozin does not represent a genotoxic risk to humans.

Dapagliflozin had no effects on mating, fertility, or early embryonic development in treated male or female rats at exposure multiples less than or equal to 1708‑times and 998‑times the maximum recommended human dose in males and females, respectively.

14 CLINICAL STUDIES

14.1 Glycemic Control in Adults with Type 2 Diabetes Mellitus

Overview of Clinical Trials of FARXIGA in Adults with Type 2 Diabetes Mellitus

FARXIGA has been studied in adult patients as monotherapy, in combination with metformin, pioglitazone, sulfonylurea (glimepiride), sitagliptin (with or without metformin), metformin plus a sulfonylurea, or insulin (with or without other oral antidiabetic therapy), compared to a sulfonylurea (glipizide), and in combination with a GLP-1 receptor agonist (exenatide extended release) added on to metformin. FARXIGA has also been studied in adult patients with type 2 diabetes mellitus and moderate renal impairment.

Treatment with FARXIGA as monotherapy and in combination with metformin, glimepiride, pioglitazone, sitagliptin, or insulin produced statistically significant improvements in mean change from baseline at Week 24 in HbA1c compared to control. Reductions in HbA1c were seen across subgroups including gender, age, race, duration of disease, and baseline body mass index (BMI).

Monotherapy

A total of 840 treatment-naive adult patients with inadequately controlled type 2 diabetes mellitus participated in 2 placebo-controlled trials to evaluate the safety and efficacy of monotherapy with FARXIGA.

In one monotherapy trial, a total of 558 treatment-naive patients with inadequately controlled diabetes participated in a 24-week trial (NCT00528372). Following a 2-week diet and exercise placebo lead-in period, 485 patients with HbA1c ≥7% and ≤10% were randomized to FARXIGA 5 mg or FARXIGA 10 mg once daily in either the morning (QAM, main cohort) or evening (QPM), or placebo.

At Week 24, treatment with FARXIGA 10 mg QAM provided significant improvements in HbA1c and the fasting plasma glucose (FPG) compared with placebo (see Table 7).

Table 7: Results at Week 24 (LOCF [LOCF: last observation (prior to rescue for rescued patients) carried forward.]) in a Placebo-Controlled Trial of FARXIGA Monotherapy in Adults with Type 2 Diabetes Mellitus (Main Cohort AM Doses)
Efficacy Parameter | FARXIGA 10 mg N=70 [All randomized patients who took at least one dose of double-blind trial medication during the short-term double-blind period.] | FARXIGA 5 mg N=64 | Placebo N=75
HbA1c (%)
Baseline (mean) | 8.0 | 7.8 | 7.8
Change from baseline (adjusted mean [Least squares mean adjusted for baseline value.]) | −0.9 | −0.8 | −0.2
Difference from placebo (adjusted mean) (95% CI) | −0.7 [p-value <0.0001 versus placebo. Sensitivity analyses yielded smaller estimates of treatment difference with placebo.] (−1.0, −0.4) | −0.5 (−0.8, −0.2)
Percent of patients achieving HbA1c <7% adjusted for baseline | 50.8% [Not evaluated for statistical significance as a result of the sequential testing procedure for the secondary endpoints.] | 44.2% | 31.6%
FPG (mg/dL)
Baseline (mean) | 166.6 | 157.2 | 159.9
Change from baseline (adjusted mean) | −28.8 | −24.1 | −4.1
Difference from placebo (adjusted mean) (95% CI) | −24.7 (−35.7, −13.6) | −19.9 (−31.3, −8.5)

Initial Combination Therapy with Metformin XR

A total of 1236 treatment-naive adult patients with inadequately controlled type 2 diabetes mellitus (HbA1c ≥7.5% and ≤12%) participated in 2 active-controlled trials of 24-week duration to evaluate initial therapy with FARXIGA 5 mg or 10 mg in combination with metformin extended-release (XR) formulation.

In one trial (NCT00859898), 638 patients randomized to 1 of 3 treatment arms following a 1-week lead-in period received: FARXIGA 10 mg plus metformin XR (up to 2,000 mg per day), FARXIGA 10 mg plus placebo, or metformin XR (up to 2,000 mg per day) plus placebo. Metformin XR dose was up-titrated weekly in 500 mg increments, as tolerated, with a median dose achieved of 2,000 mg.

The combination treatment of FARXIGA 10 mg plus metformin XR provided statistically significant improvements in HbA1c and FPG compared with either of the monotherapy treatments and statistically significant reduction in body weight compared with metformin XR alone (see Table 8 and Figure 2). FARXIGA 10 mg as monotherapy also provided statistically significant improvements in FPG and statistically significant reduction in body weight compared with metformin alone and was non inferior to metformin XR monotherapy in lowering HbA1c

Table 8: Results at Week 24 (LOCF1) in an Active-Controlled Trial of FARXIGA Initial Combination Therapy with Metformin XR
Efficacy Parameter | FARXIGA 10 mg + Metformin XR | FARXIGA 10 mg | Metformin XR
 | N=211 [All randomized patients who took at least one dose of double-blind trial medication during the short-term double-blind period.] | N=219 | N=208
HbA1c (%)
Baseline (mean) | 9.1 | 9.0 | 9.0
Change from baseline (adjusted mean [Least squares mean adjusted for baseline value.]) | −2.0 | −1.5 | −1.4
Difference from FARXIGA (adjusted mean) (95% CI) | −0.5 [p-value <0.0001.] (−0.7, −0.3)
Difference from metformin XR (adjusted mean) (95% CI) | −0.5 (−0.8, −0.3) | 0.0 [Non-inferior versus metformin XR.] (−0.2, 0.2)
Percent of patients achieving HbA1c <7% adjusted for baseline | 46.6% [p-value <0.05.] | 31.7% | 35.2%
FPG (mg/dL)
Baseline (mean) | 189.6 | 197.5 | 189.9
Change from baseline (adjusted mean) | −60.4 | −46.4 | −34.8
Difference from FARXIGA (adjusted mean) (95% CI) | −13.9 (−20.9, −7.0)
Difference from metformin XR (adjusted mean) (95% CI) | −25.5 (−32.6, −18.5) | −11.6 (−18.6, −4.6)
Body Weight (kg)
Baseline (mean) | 88.6 | 88.5 | 87.2
Change from baseline (adjusted mean) | −3.3 | −2.7 | −1.4
Difference from metformin XR (adjusted mean) (95% CI) | −2.0 (−2.6, −1.3) | −1.4; (−2.0, −0.7)

Figure 2: Adjusted Mean Change from Baseline Over Time in HbA1c (%) in a 24-Week Active-Controlled Trial of FARXIGA Initial Combination Therapy with Metformin XR

In a second trial (NCT00643851), 603 patients were randomized to 1 of 3 treatment arms following a 1-week lead-in period: FARXIGA 5 mg plus metformin XR (up to 2,000 mg per day), FARXIGA 5 mg plus placebo, or metformin XR (up to 2,000 mg per day) plus placebo. Metformin XR dose was up-titrated weekly in 500 mg increments, as tolerated, with a median dose achieved of 2,000 mg.

The combination treatment of FARXIGA 5 mg plus metformin XR provided statistically significant improvements in HbA1c and FPG compared with either of the monotherapy treatments and statistically significant reduction in body weight compared with metformin XR alone (see Table 9).

Table 9: Results at Week 24 (LOCF [LOCF: last observation (prior to rescue for rescued patients) carried forward.]) in an Active-Controlled Trial of FARXIGA Initial Combination Therapy with Metformin XR
Efficacy Parameter | FARXIGA 5 mg + Metformin XR | FARXIGA 5 mg | Metformin; XR
 | N=194 [All randomized patients who took at least one dose of double-blind trial medication during the short-term double-blind period.] | N=203 | N=201
HbA1c (%)
Baseline (mean) | 9.2 | 9.1 | 9.1
Change from baseline (adjusted mean [Least squares mean adjusted for baseline value.]) | −2.1 | −1.2 | −1.4
Difference from FARXIGA (adjusted mean) (95% CI) | −0.9 [p-value <0.0001.] (−1.1, −0.6)
Difference from metformin XR (adjusted mean) (95% CI) | −0.7 (-0.9, -0.5)
Percent of patients achieving HbA1c <7% adjusted for baseline | 52.4% [p-value <0.05.] | 22.5% | 34.6%
FPG (mg/dL)
Baseline (mean) | 193.4 | 190.8 | 196.7
Change from baseline (adjusted mean) | -61.0 | -42.0 | -33.6
Difference from FARXIGA (adjusted mean) (95% CI) | -19.1 (-26.7, -11.4)
Difference from metformin XR (adjusted mean) (95% CI) | -27.5 (-35.1, -19.8)
Body Weight (kg)
Baseline (mean) | 84.2 | 86.2 | 85.8
Change from baseline (adjusted mean) | -2.7 | -2.6 | -1.3
Difference from metformin XR (adjusted mean) (95% CI) | -1.4 (-2.0, -0.7)

Add-On to Metformin

A total of 546 adult patients with type 2 diabetes mellitus with inadequate glycemic control (HbA1c ≥7% and ≤10%) participated in a 24-week, placebo-controlled trial to evaluate FARXIGA in combination with metformin (NCT00528879). Patients on metformin at a dose of at least 1,500 mg per day were randomized after completing a 2-week, single-blind, placebo lead-in period. Following the lead-in period, eligible patients were randomized to FARXIGA 5 mg, FARXIGA 10 mg, or placebo in addition to their current dose of metformin.

As add-on treatment to metformin, FARXIGA 10 mg provided statistically significant improvements in HbA1c and FPG, and statistically significant reduction in body weight compared with placebo at Week 24 (see Table 10 and Figure 3). Statistically significant (p <0.05 for both doses) mean changes from baseline in systolic blood pressure relative to placebo plus metformin were −4.5 mmHg and −5.3 mmHg with FARXIGA 5 mg and 10 mg plus metformin, respectively.

Table 10: Results of a 24-Week (LOCF [LOCF: last observation (prior to rescue for rescued patients) carried forward.]) Placebo-Controlled Trial of FARXIGA in Add-On Combination with Metformin
Efficacy Parameter | FARXIGA 10 mg + Metformin N=135 [All randomized patients who took at least one dose of double-blind study medication during the short-term double-blind period.] | FARXIGA 5 mg + Metformin N=137 | Placebo + Metformin N=137
HbA1c (%)
Baseline (mean) | 7.9 | 8.2 | 8.1
Change from baseline (adjusted mean [Least squares mean adjusted for baseline value.]) | -0.8 | -0.7 | -0.3
Difference from placebo (adjusted mean) (95% CI) | -0.5 [p-value <0.0001 versus placebo + metformin.]; (-0.7, -0.3) | -0.4; (-0.6, -0.2)
Percent of patients achieving HbA1c <7% adjusted for baseline | 40.6% [p-value <0.05 versus placebo + metformin.] | 37.5% | 25.9%
FPG (mg/dL)
Baseline (mean) | 156.0 | 169.2 | 165.6
Change from baseline at Week 24 (adjusted mean) | -23.5 | -21.5 | -6.0
Difference from placebo (adjusted mean) (95% CI) | -17.5 (-25.0, -10.0) | -15.5 (-22.9, -8.1)
Change from baseline at Week 1 (adjusted mean) | -16.5 (N=115) | -12.0 (N=121) | 1.2 (N=126)
Body Weight (kg)
Baseline (mean) | 86.3 | 84.7 | 87.7
Change from baseline (adjusted mean) | -2.9 | -3.0 | -0.9
Difference from placebo (adjusted mean); (95% CI) | -2.0 (-2.6, -1.3) | -2.2; (-2.8, -1.5)

Figure 3: Adjusted Mean Change from Baseline Over Time in HbA1c (%) in a 24-Week Placebo-Controlled Study of FARXIGA in Combination with Metformin

Active Glipizide-Controlled Study Add-On to Metformin

A total of 816 adult patients with type 2 diabetes mellitus with inadequate glycemic control (HbA1c >6.5% and ≤10%) were randomized in a 52-week, glipizide-controlled, non-inferiority trial to evaluate FARXIGA as add-on therapy to metformin (NCT00660907). Patients on metformin at a dose of at least 1,500 mg per day were randomized following a 2-week placebo lead-in period to glipizide or dapagliflozin (5 mg or 2.5 mg, respectively) and were up-titrated over 18 weeks to optimal glycemic effect (FPG <110 mg/dL, <6.1 mmol/L) or to the highest dose level (up to glipizide 20 mg and FARXIGA 10 mg) as tolerated by patients. Thereafter, doses were kept constant, except for down-titration to prevent hypoglycemia.

At the end of the titration period, 87% of patients treated with FARXIGA had been titrated to the maximum trial dose (10 mg) versus 73% treated with glipizide (20 mg). FARXIGA led to a similar mean reduction in HbA1c from baseline at Week 52 (LOCF), compared with glipizide, thus demonstrating non inferiority (see Table 11). FARXIGA treatment led to a statistically significant mean reduction in body weight from baseline at Week 52 (LOCF) compared with a mean increase in body weight in the glipizide group. Statistically significant (p<0.0001) mean change from baseline in systolic blood pressure relative to glipizide plus metformin was 5.0 mmHg with FARXIGA plus metformin.

Table 11: Results at Week 52 (LOCF [LOCF: last observation carried forward.]) in an Active-Controlled Study Comparing FARXIGA to Glipizide as Add-On to Metformin
Efficacy Parameter | FARXIGA + Metformin N=400 [Randomized and treated patients with baseline and at least 1 post-baseline efficacy measurement.] | Glipizide + Metformin N=401
HbA1c (%)
Baseline (mean) | 7.7 | 7.7
Change from baseline (adjusted mean [Least squares mean adjusted for baseline value.]) | -0.5 | -0.5
Difference from glipizide + metformin (adjusted mean) (95% CI) | 0.0 [Non-inferior to glipizide + metformin.] (-0.1, 0.1)
Body Weight (kg)
Baseline (mean) | 88.4 | 87.6
Change from baseline (adjusted mean) | -3.2 | 1.4
Difference from glipizide + metformin (adjusted mean) (95% CI) | -4.7 [p-value <0.0001.] (-5.1, -4.2)

Add-On Combination Therapy with Other Antidiabetic Agents

Add-On Combination Therapy with a Sulfonylurea

A total of 597 adult patients with type 2 diabetes mellitus and inadequate glycemic control (HbA1c ≥7% and ≤10%) were randomized in this 24-week, placebo-controlled trial to evaluate FARXIGA in combination with glimepiride (a sulfonylurea) (NCT00680745).

Patients on at least half the maximum recommended dose of glimepiride as monotherapy (4 mg) for at least 8 weeks lead-in were randomized to FARXIGA 5 mg, FARXIGA 10 mg, or placebo in addition to glimepiride 4 mg per day. Down-titration of glimepiride to 2 mg or 0 mg was allowed for hypoglycemia during the treatment period; no up-titration of glimepiride was allowed.

In combination with glimepiride, FARXIGA 10 mg provided statistically significant improvement in HbA1c, FPG, and 2-hour PPG, and statistically significant reduction in body weight compared with placebo plus glimepiride at Week 24 (see Table 12). Statistically significant (p<0.05 for both doses) mean changes from baseline in systolic blood pressure relative to placebo plus glimepiride were −2.8 mmHg and −3.8 mmHg with FARXIGA 5 mg and 10 mg plus glimepiride, respectively.

Add-on Combination Therapy with Metformin and a Sulfonylurea

A total of 218 adult patients with type 2 diabetes mellitus and inadequate glycemic control (HbA1c ≥7% and ≤10.5%) participated in a 24-week, placebo-controlled trial to evaluate FARXIGA in combination with metformin and a sulfonylurea (NCT01392677). Patients on a stable dose of metformin (immediate- or extended-release formulations) ≥1,500 mg/day plus maximum tolerated dose, which must be at least half the maximum dose, of a sulfonylurea for at least 8 weeks prior to enrollment were randomized after an 8-week placebo lead-in period to FARXIGA 10 mg or placebo. Dose-titration of FARXIGA or metformin was not permitted during the 24-week treatment period. Down-titration of the sulfonylurea was permitted to prevent hypoglycemia, but no up-titration was permitted. As add-on treatment to combined metformin and a sulfonylurea, treatment with FARXIGA 10 mg provided statistically significant improvements in HbA1c and FPG and statistically significant reduction in body weight compared with placebo at Week 24 (Table 12). A statistically significant (p <0.05) mean change from baseline in systolic blood pressure relative to placebo in combination with metformin and a sulfonylurea was -3.8 mmHg with FARXIGA 10 mg in combination with metformin and a sulfonylurea at Week 8.

Add-On Combination Therapy with a Thiazolidinedione

A total of 420 adult patients with type 2 diabetes mellitus with inadequate glycemic control (HbA1c ≥7% and ≤10.5%) participated in a 24-week, placebo-controlled trial to evaluate FARXIGA in combination with pioglitazone [a thiazolidinedione (TZD)] alone (NCT00683878). Patients on a stable dose of pioglitazone of 45 mg per day (or 30 mg per day, if 45 mg per day was not tolerated) for 12 weeks were randomized after a 2-week lead-in period to 5 or 10 mg of FARXIGA or placebo in addition to their current dose of pioglitazone. Dose titration of FARXIGA or pioglitazone was not permitted during the trial.

In combination with pioglitazone, treatment with FARXIGA 10 mg provided statistically significant improvements in HbA1c, 2-hour PPG, FPG, the proportion of patients achieving HbA1c <7%, and a statistically significant reduction in body weight compared with the placebo plus pioglitazone treatment groups (see Table 12) at Week 24. A statistically significant (p <0.05) mean change from baseline in systolic blood pressure relative to placebo in combination with pioglitazone was −4.5 mmHg with FARXIGA 10 mg in combination with pioglitazone.

Add-On Combination Therapy with a DPP4 Inhibitor

A total of 452 adult patients with type 2 diabetes mellitus who were drug naive, or who were treated at entry with metformin or a DPP4 inhibitor alone or in combination, and had inadequate glycemic control (HbA1c ≥7.0% and ≤10.0% at randomization), participated in a 24-week, placebo-controlled trial to evaluate FARXIGA in combination with sitagliptin (a DPP4 inhibitor) with or without metformin (NCT00984867).

Eligible patients were stratified based on the presence or absence of background metformin (≥1,500 mg per day), and within each stratum were randomized to either FARXIGA 10 mg plus sitagliptin 100 mg once daily, or placebo plus sitagliptin 100 mg once daily. Endpoints were tested for FARXIGA 10 mg versus placebo for the total trial group (sitagliptin with and without metformin) and for each stratum (sitagliptin alone or sitagliptin with metformin). Thirty-seven percent (37%) of patients were drug naive, 32% were on metformin alone, 13% were on a DPP4 inhibitor alone, and 18% were on a DPP4 inhibitor plus metformin. Dose titration of FARXIGA, sitagliptin, or metformin was not permitted during the trial.

In combination with sitagliptin (with or without metformin), FARXIGA 10 mg provided statistically significant improvements in HbA1c, FPG, and a statistically significant reduction in body weight compared with the placebo plus sitagliptin (with or without metformin) group at Week 24 (see Table 12). These improvements were also seen in the stratum of patients who received FARXIGA 10 mg plus sitagliptin alone (placebo-corrected mean change for HbA1c −0.56%; n=110) compared with placebo plus sitagliptin alone (n=111), and the stratum of patients who received FARXIGA 10 mg plus sitagliptin and metformin (placebo-corrected mean change for HbA1c −0.40; n=113) compared with placebo plus sitagliptin with metformin (n=113).

Add-On Combination Therapy with Insulin

A total of 808 adult patients with type 2 diabetes mellitus who had inadequate glycemic control (HbA1c ≥7.5% and ≤10.5%) were randomized in a 24-week, placebo-controlled trial to evaluate FARXIGA as add-on therapy to insulin (NCT00673231). Patients on a stable insulin regimen, with a mean dose of at least 30 IU of injectable insulin per day, for a period of at least 8 weeks prior to enrollment and on a maximum of 2 oral antidiabetic medications (OADs), including metformin, were randomized after completing a 2-week enrollment period to receive either FARXIGA 5 mg, FARXIGA 10 mg, or placebo in addition to their current dose of insulin and other OADs, if applicable. Patients were stratified according to the presence or absence of background OADs. Up- or down-titration of insulin was only permitted during the treatment phase in patients who failed to meet specific glycemic goals. Dose modifications of blinded trial medication or OAD(s) were not allowed during the treatment phase, with the exception of decreasing OAD(s) where there were concerns over hypoglycemia after cessation of insulin therapy.

In this trial, 50% of patients were on insulin monotherapy at baseline, while 50% were on 1 or 2 OADs in addition to insulin. At Week 24, FARXIGA 10 mg dose provided statistically significant improvement in HbA1c and reduction in mean insulin dose, and a statistically significant reduction in body weight compared with placebo in combination with insulin, with or without up to 2 OADs (see Table 12); the effect of FARXIGA on HbA1c was similar in patients treated with insulin alone and patients treated with insulin plus OAD. Statistically significant (p<0.05) mean change from baseline in systolic blood pressure relative to placebo in combination with insulin was −3.0 mmHg with FARXIGA 10 mg in combination with insulin.

At Week 24, FARXIGA 5 mg (−5.7 IU, difference from placebo) and 10 mg (−6.2 IU, difference from placebo) once daily resulted in a statistically significant reduction in mean daily insulin dose (p<0.0001 for both doses) compared to placebo in combination with insulin, and a statistically significantly higher proportion of patients on FARXIGA 10 mg (19.6%) reduced their insulin dose by at least 10% compared to placebo (11.0%).

Table 12: Results of 24-Week (LOCF [LOCF: last observation (prior to rescue for rescued patients) carried forward.]) Placebo-Controlled Trials of FARXIGA in Combination with Antidiabetic Agents
Efficacy Parameter | FARXIGA 10 mg | FARXIGA 5 mg | Placebo
In Combination with Sulfonylurea (Glimepiride)
Intent-to-Treat Population | N=151 [Randomized and treated patients with baseline and at least 1 post-baseline efficacy measurement.] | N=142 | N=145
HbA1c (%)
Baseline (mean) | 8.1 | 8.1 | 8.2
Change from baseline (adjusted mean [Least squares mean adjusted for baseline value based on an ANCOVA model.]) | -0.8 | -0.6 | -0.1
Difference from placebo (adjusted mean) (95% CI) | -0.7 [p-value <0.0001 versus placebo.]; (-0.9, -0.5) | -0.5; (-0.7, -0.3)
Percent of patients achieving HbA1c <7% adjusted for baseline | 31.7% | 30.3% | 13.0%
FPG (mg/dL)
Baseline (mean) | 172.4 | 174.5 | 172.7
Change from baseline (adjusted mean) | -28.5 | -21.2 | -2.0
Difference from placebo (adjusted mean); (95% CI) | -26.5; (-33.5, -19.5) | -19.3; (-26.3, -12.2)
2-hour PPG [2-hour PPG level as a response to a 75-gram oral glucose tolerance test (OGTT).] (mg/dL)
Baseline (mean) | 329.6 | 322.8 | 324.1
Change from baseline (adjusted mean) | -60.6 | –54.5 | -11.5
Difference from placebo (adjusted mean); (95% CI) | -49.1; (-64.1, -34.1) | -43.0; (–58.4, -27.5)
Body Weight (kg)
Baseline (mean) | 80.6 | 81.0 | 80.9
Change from baseline (adjusted mean) | -2.3 | -1.6 | -0.7
Difference from placebo (adjusted mean); (95% CI) | -1.5; (-2.2, -0.9) | -0.8; (-1.5, -0.2)
In Combination with Metformin and a Sulfonylurea
Intent-to-Treat Population | N=108 | - | N=108
HbA1c (%)
Baseline (mean) | 8.08 | - | 8.24
Change from baseline (adjusted mean [Least squares mean adjusted for baseline value based on a longitudinal repeated measures model.]) | -0.86 | - | -0.17
Difference from placebo (adjusted mean); (95% CI) | -0.69; (-0.89, -0.49) | -
Percent of patients achieving HbA1c <7% adjusted for baseline | 31.8% | - | 11.1%
FPG (mg/dL)
Baseline (mean) | 167.4 | - | 180.3
Change from baseline (adjusted mean) | -34.2 | - | -0.8
Difference from placebo (adjusted mean); (95% CI) | -33.5; (-43.1, -23.8) | -
Body Weight (kg)
Baseline (mean) | 88.57 | - | 90.07
Change from baseline (adjusted mean) | -2.65 | - | -0.58
Difference from placebo (adjusted mean); (95% CI) | -2.07; (-2.79, -1.35) | -
In Combination with Thiazolidinedione (Pioglitazone)
Intent-to-Treat Population | N=140 [All randomized patients who took at least one dose of double-blind study medication during the short-term, double-blind period.] | N=141 | N=139
HbA1c (%)
Baseline (mean) | 8.4 | 8.4 | 8.3
Change from baseline (adjusted mean) | -1.0 | -0.8 | -0.4
Difference from placebo (adjusted mean); (95% CI) | -0.6; (-0.8, -0.3) | -0.4; (-0.6, -0.2)
Percent of patients achieving HbA1c <7% adjusted for baseline | 38.8% [p-value <0.05 versus placebo.] | 32.5% | 22.4%
FPG (mg/dL)
Baseline (mean) | 164.9 | 168.3 | 160.7
Change from baseline (adjusted mean) | -29.6 | -24.9 | -5.5
Difference from placebo (adjusted mean); (95% CI) | -24.1; (-32.2, -16.1) | -19.5; (-27.5, -11.4)
2-hour PPG (mg/dL)
Baseline (mean) | 308.0 | 284.8 | 293.6
Change from baseline (adjusted mean) | -67.5 | -65.1 | -14.1
Difference from placebo (adjusted mean); (95% CI) | -53.3; (-71.1, -35.6) | -51.0; (-68.7, -33.2)
Body Weight (kg)
Baseline (mean) | 84.8 | 87.8 | 86.4
Change from baseline (adjusted mean) | -0.1 | 0.1 | 1.6
Difference from placebo (adjusted mean); (95% CI) | -1.8; (-2.6, -1.0) | -1.6; (-2.3, -0.8)
In Combination with DPP4 Inhibitor (Sitagliptin) with or without Metformin
Intent-to-Treat Population | N=223 | – | N=224
HbA1c (%)
Baseline (mean) | 7.90 | – | 7.97
Change from baseline (adjusted mean) | -0.45 | – | 0.04
Difference from placebo (adjusted mean); (95% CI) | -0.48; (-0.62, -0.34) | –
Patients with HbA1c decrease ≥0.7% (adjusted percent) | 35.4% | – | 16.6%
FPG (mg/dL)
Baseline (mean) | 161.7 | – | 163.1
Change from baseline at Week 24 (adjusted mean) | -24.1 | – | 3.8
Difference from placebo (adjusted mean); (95% CI) | -27.9; (-34.5, -21.4) | –
Body Weight (kg)
Baseline (mean) | 91.02 | – | 89.23
Change from baseline (adjusted mean) | -2.14 | – | -0.26
Difference from placebo (adjusted mean); (95% CI) | -1.89; (-2.37, -1.40) | –
In Combination with Insulin with or without up to 2 Oral Antidiabetic Therapies
Intent-to-Treat Population | N=194 | N=211 | N=193
HbA1c (%)
Baseline (mean) | 8.6 | 8.6 | 8.5
Change from baseline (adjusted mean) | -0.9 | -0.8 | -0.3
Difference from placebo (adjusted mean); (95% CI) | -0.6; (-0.7, -0.5) | -0.5; (-0.7, -0.4)
FPG (mg/dL)
Baseline (mean) | 173.7 | NT [NT: Not formally tested because of failing to achieve a statistically significant difference in an endpoint that was earlier in the testing sequence.] | 170.0
Change from baseline (adjusted mean) | -21.7 | NT | 3.3
Difference from placebo (adjusted mean); (95% CI) | -25.0; (-34.3, -15.8) | NT
Body Weight (kg)
Baseline (mean) | 94.6 | 93.2 | 94.2
Change from baseline (adjusted mean) | -1.7 | -1.0 | 0.0
Difference from placebo (adjusted mean); (95% CI) | -1.7; (-2.2, -1.2) | -1.0; (-1.5, -0.5)

Combination Therapy with Exenatide-Extended Release as Add-On to Metformin

A total of 694 adult patients with type 2 diabetes mellitus and inadequate glycemic control (HbA1c ≥8.0 and ≤12.0%) on metformin, were evaluated in a 28-week double-blind, active-controlled trial to compare FARXIGA in combination with exenatide extended-release (a GLP 1 receptor agonist) to FARXIGA alone and exenatide extended-release alone, as add on to metformin (NCT02229396). Patients on metformin at a dose of at least 1,500 mg per day were randomized following a 1-week placebo lead-in period to receive either FARXIGA 10 mg once daily (QD) in combination with exenatide extended release 2 mg once weekly (QW), FARXIGA 10 mg QD, or exenatide extended–release 2 mg QW.

At Week 28, FARXIGA in combination with exenatide extended-release provided statistically significantly greater reductions in HbA1c (-1.77%) compared to FARXIGA alone (-1.32%, p=0.001) and exenatide extended-release alone (-1.42%, p=0.012). FARXIGA in combination with exenatide extended-release provided statistically significantly greater reductions in FPG (-57.35 mg/dL) compared to FARXIGA alone (-44.72 mg/dL, p=0.006) and exenatide extended-release alone (-40.53, p <0.001).

Use in Adults with Type 2 Diabetes Mellitus and Moderate Renal Impairment

FARXIGA was assessed in two placebo-controlled trials of adult patients with type 2 diabetes mellitus and moderate renal impairment.

Patients with type 2 diabetes mellitus and an eGFR between 45 to less than 60 mL/min/1.73 m^2 inadequately controlled on current diabetes therapy participated in a 24-week, double-blind, placebo-controlled clinical trial (NCT02413398). Patients were randomized to either FARXIGA 10 mg or placebo, administered orally once daily. At Week 24, FARXIGA provided statistically significant reductions in HbA1c compared with placebo (Table 13).

Table 13: Results at Week 24 of Placebo-Controlled Trial for FARXIGA in Adults with Type 2 Diabetes Mellitus and Renal Impairment (eGFR 45 to less than 60 mL/min/1.73 m^2)

 | FARXIGA 10 mg | Placebo
Number of patients: | N=160 | N=161
HbA1c (%)
Baseline (mean) | 8.3 | 8.0
Change from baseline (adjusted mean [Least squares mean adjusted for baseline value; at Week 24, HbA1c was missing for 5.6% and 6.8% of individuals treated with FARXIGA and placebo, respectively. Retrieved dropouts, i.e., observed HbA1c at Week 24 from subjects who discontinued treatment, were used to impute missing values in HbA1c.]) | -0.4 | -0.1
Difference from placebo (adjusted mean); (95% CI) | -0.3 [p-value =0.008 versus placebo.]; (-0.5, - 0.1)

14.2 Glycemic Control in Pediatric Patients Aged 10 Years and Older with Type 2 Diabetes Mellitus

In a pediatric trial (NCT03199053), patients aged 10 to 17 years with inadequately controlled type 2 diabetes mellitus (HbA1c ≥6.5% and ≤10.5%) were randomized to FARXIGA (81 patients) or placebo (76 patients) as add-on to metformin, insulin or a combination of metformin and insulin. In this 26-week, placebo-controlled, double-blind randomized clinical trial with a 26-week safety extension, patients received 5 mg of FARXIGA or placebo following a lead-in period. At Week 14, patients with HbA1c values <7% remained on 5 mg while patients with HbA1c values ≥7% were randomized to either continue on 5 mg or up titrate to 10 mg.

At baseline, 88% of FARXIGA-treated patients and 89% of placebo-treated patients were on metformin with or without insulin as background medication. The mean HbA1c at baseline was 8.2% in FARXIGA-treated patients and 8.0% in placebo-treated patients, and the mean duration of type 2 diabetes mellitus was 2.3 years in FARXIGA-treated patients and 2.5 years in placebo-treated patients. The mean age was 14.4 years in FARXIGA-treated patients and 14.7 years in placebo-treated patients, and approximately 61% of FARXIGA-treated patients and 58% of placebo-treated patients were female. In FARXIGA-treated patients, approximately 52% were White, 22% were Asian, 9% were Black or African American, and 56% were of Hispanic or Latino ethnicity. In placebo-treated patients, approximately 42% were White, 32% were Asian, 4% were Black or African American, and 45% were of Hispanic or Latino ethnicity. The mean BMI was 29.7 kg/m^2 in FARXIGA-treated patients and 28.5 kg/m2 in placebo-treated patients, and mean BMI Z-score was 1.7 in FARXIGA-treated patients and 1.5 in placebo-treated patients. The mean eGFR at baseline was 115 mL/min/1.73 m^2 in FARXIGA-treated patients and 113 mL/min/1.73 m^2 in placebo-treated patients.

At Week 26, treatment with FARXIGA provided statistically significant improvements in HbA1c compared with placebo (Table 14). This effect was consistent across subgroups including race, ethnicity, sex, age group (≥10 to <15 years of age and ≥15 to <18 years of age), background antidiabetic treatment, and baseline BMI.

Table 14: Results at Week 26 in a Placebo-Controlled Trial of FARXIGA as Add-On to Metformin and/or Insulin in Pediatric Patients Aged 10 Years and Older with Type 2 Diabetes Mellitus
Efficacy Parameter | FARXIGA 5 mg and 10 mg | Placebo
Intent-to-Treat Population (N) [All randomized patients who received at least one dose of double-blind trial medication during the treatment period. Includes data regardless of rescue or premature treatment discontinuation.] | 81 | 76
HbA1c (%)
Baseline (mean) | 8.2 | 8.0
Change from baseline (adjusted mean [Multiple imputations using placebo washout approach for missing efficacy endpoint. Imputed for HbA1c (FARXIGA N=6 (7.4%), placebo N=6 (7.9%)), for FPG (FARXIGA N=6 (7.4%), placebo N=8 (10.5%)).]) | -0.6 | 0.4
Difference from placebo (adjusted mean) (95% CI) | -1.0 [Least squares mean adjusted for baseline value, treatment, age, gender and baseline diabetic medication.]; (-1.6, -0.5)
FPG (mg/dL)
Baseline (mean) | 162.2 | 152.1
Change from baseline (adjusted mean) | -10.3 | 9.2
Difference from placebo (adjusted mean); (95% CI) | -19.5 [p-value versus placebo <0.001. p-value is two-sided.]; (-36.4, -2.5)
Percent of subjects with Baseline HbA1c ≥7% Achieving a HbA1c Level <7% | 26.6%; (N [p-value versus placebo <0.05. p-value is two-sided.] =64) | 10.0%; (N=50)
CI=confidence interval

14.3 Cardiovascular Outcomes in Adults with Type 2 Diabetes Mellitus

Dapagliflozin Effect on Cardiovascular Events (DECLARE, NCT01730534) was an international, multicenter, randomized, double-blind, placebo-controlled, clinical trial conducted to determine the effect of FARXIGA relative to placebo on cardiovascular (CV) outcomes when added to current background therapy. All patients had type 2 diabetes mellitus and either established CV disease or two or more additional CV risk factors (age ≥55 years in men or ≥60 years in women and one or more of dyslipidemia, hypertension, or current tobacco use). Concomitant antidiabetic and atherosclerotic therapies could be adjusted, at the discretion of investigators, to ensure participants were treated according to the standard care for these diseases.

Of 17160 randomized patients, 6974 (40.6%) had established CV disease and 10186 (59.4%) did not have established CV disease. A total of 8582 patients were randomized to FARXIGA 10 mg, 8578 to placebo, and patients were followed for a median of 4.2 years.

Approximately 80% of the trial population was White, 4% Black or African American, and 13% Asian. The mean age was 64 years, and approximately 63% were male.

Mean duration of diabetes was 11.9 years and 22.4% of patients had diabetes for less than 5 years. Mean eGFR was 85.2 mL/min/1.73 m^2. At baseline, 23.5% of patients had microalbuminuria (UACR ≥30 to ≤300 mg/g) and 6.8% had macroalbuminuria (UACR >300 mg/g). Mean HbA1c was 8.3% and mean BMI was 32.1 kg/m^2. At baseline, 10% of patients had a history of heart failure.

Most patients (98.1%) used one or more antihyperglycemic medications at baseline. 82.0% of the patients were being treated with metformin, 40.9% with insulin, 42.7% with a sulfonylurea, 16.8% with a DPP4 inhibitor, and 4.4% with a GLP-1 receptor agonist.

Approximately 81.3% of patients were treated with angiotensin converting enzyme inhibitors or angiotensin receptor blockers, 75.0% with statins, 61.1% with antiplatelet therapy, 55.5% with acetylsalicylic acid, 52.6% with beta-blockers, 34.9% with calcium channel blockers, 22.0% with thiazide diuretics, and 10.5% with loop diuretics.

A Cox proportional hazards model was used to test for non-inferiority against the pre-specified risk margin of 1.3 for the hazard ratio (HR) of the composite of CV death, myocardial infarction (MI), or ischemic stroke (MACE) and if non-inferiority was demonstrated, to test for superiority on the two primary endpoints: 1) the composite of hospitalization for heart failure or CV death, and 2) MACE.

The incidence rate of MACE was similar in both treatment arms: 2.30 MACE events per 100 patient-years on dapagliflozin vs 2.46 MACE events per 100 patient-years on placebo. The estimated hazard ratio of MACE associated with dapagliflozin relative to placebo was 0.93 with a 95% CI of (0.84, 1.03). The upper bound of this confidence interval, 1.03, excluded the pre-specified non-inferiority margin of 1.3.

FARXIGA was superior to placebo in reducing the incidence of the primary composite endpoint of hospitalization for heart failure or CV death [HR 0.83 (95% CI 0.73, 0.95)].

The treatment effect was due to a significant reduction in the risk of hospitalization for heart failure in subjects randomized to FARXIGA [HR 0.73 (95% CI 0.61, 0.88)], with no change in the risk of CV death (Table 15 and Figures 4 and 5).

Table 15: Treatment Effects for the Primary Endpoints [Full analysis set.] and their Components in the DECLARE Study
 | Patients with events n (%)
Efficacy Variable; (time to first occurrence) | FARXIGA 10 mg; N=8582 | Placebo; N=8578 | Hazard ratio; (95% CI)
Primary Endpoints
Composite of Hospitalization for Heart Failure, CV Death [p-value =0.005 versus placebo.] | 417 (4.9) | 496 (5.8) | 0.83 (0.73, 0.95)
Composite Endpoint of CV Death, MI, Ischemic Stroke | 756 (8.8) | 803 (9.4) | 0.93 (0.84, 1.03)
Components of the composite endpoints [Total number of events presented for each component of the composite endpoints.]
Hospitalization for Heart Failure | 212 (2.5) | 286 (3.3) | 0.73 (0.61, 0.88)
CV Death | 245 (2.9) | 249 (2.9) | 0.98 (0.82, 1.17)
Myocardial Infarction | 393 (4.6) | 441 (5.1) | 0.89 (0.77, 1.01)
Ischemic Stroke | 235 (2.7) | 231 (2.7) | 1.01 (0.84, 1.21)
N=Number of patients, CI=Confidence interval, CV=Cardiovascular, MI=Myocardial infarction.

Figure 4: Time to First Occurrence of Hospitalization for Heart Failure or CV Death in the DECLARE Study

Figure 5: Time to First Occurrence of Hospitalization for Heart Failure in the DECLARE Study

14.4 Chronic Kidney Disease

The Trial to Evaluate the Effect of Dapagliflozin on Renal Outcomes and Cardiovascular Mortality in Patients with Chronic Kidney Disease (DAPA-CKD, NCT03036150) was an international, multicenter, randomized, double-blind, placebo-controlled trial in adult patients with chronic kidney disease (CKD) (eGFR between 25 and 75 mL/min/1.73 m^2) and albuminuria [urine albumin creatinine ratio (UACR) between 200 and 5000 mg/g] who were receiving standard of care background therapy, including a maximally tolerated, labeled daily dose of an angiotensin-converting enzyme inhibitor (ACEi) or angiotensin receptor blocker (ARB). The trial excluded patients with autosomal dominant or autosomal recessive polycystic kidney disease, lupus nephritis, or ANCA-associated vasculitis and patients requiring cytotoxic, immunosuppressive, or immunomodulatory therapies in the preceding 6 months.

The primary objective was to determine whether FARXIGA reduces the incidence of the composite endpoint of ≥50% sustained decline in eGFR, progression to end stage kidney disease (ESKD) (defined as sustained eGFR <15 mL/min/1.73 m^2, initiation of chronic dialysis treatment or renal transplant), CV or renal death.

A total of 4304 patients were randomized equally to FARXIGA 10 mg or placebo and were followed for a median of 28.5 months.

The mean age of the trial population was 62 years and 67% were male. The population was 53% White, 4% Black or African American, and 34% Asian; 25% were of Hispanic or Latino ethnicity.

At baseline, mean eGFR was 43 mL/min/1.73 m^2, 44% of patients had an eGFR 30 mL/min/1.73 m^2 to less than 45 mL/min/1.73 m^2, and 15% of patients had an eGFR less than 30 mL/min/1.73 m^2. Median UACR was 950 mg/g. A total of 68% of the patients had type 2 diabetes mellitus at randomization. The most common etiologies of CKD were diabetic nephropathy (58%), ischemic/hypertensive nephropathy (16%), and IgA nephropathy (6%).

At baseline, 97% of patients were treated with ACEi or ARB. Approximately 44% were taking antiplatelet agents, and 65% were on a statin.

FARXIGA reduced the incidence of the primary composite endpoint of ≥50% sustained decline in eGFR, progression to ESKD, CV or renal death [HR 0.61 (95% CI 0.51,0.72); p<0.0001]. The FARXIGA and placebo event curves separate by Month 4 and continue to diverge over the trial period. The treatment effect reflected a reduction in ≥50% sustained decline in eGFR, progression to ESKD, and CV death. There were few renal deaths during the trial (Table 16, Figure 6).

FARXIGA also reduced the incidence of the composite endpoint of CV death or hospitalization for heart failure [HR 0.71 (95% CI 0.55, 0.92), p=0.0089] and all-cause mortality [HR 0.69 (95% CI 0.53, 0.88), p=0.0035].

Table 16: Treatment Effect for the Primary Composite Endpoint, its Components, and Secondary Composite Endpoints, in the DAPA-CKD Study
 | Patients with events (event rate)
Efficacy Variable; (time to first occurrence) | FARXIGA 10 mg N=2152 | Placebo N=2152 | Hazard ratio (95% CI) | p-value
Composite of ≥50% sustained eGFR decline, ESKD, CV or renal death | 197 (4.6) | 312 (7.5) | 0.61 (0.51, 0.72) | <0.0001
≥50% sustained eGFR decline | 112 (2.6) | 201 (4.8) | 0.53 (0.42, 0.67)
ESKD [ESKD is defined as sustained eGFR <15 mL/min/1.73 m^2, initiation of chronic dialysis treatment, or transplant.] | 109 (2.5) | 161 (3.8) | 0.64 (0.50, 0.82)
CV Death | 65 (1.4) | 80 (1.7) | 0.81 (0.58, 1.12)
Renal Death | 2 (<0.1) | 6 (0.1)
≥50% sustained eGFR decline, ESKD or renal death | 142 (3.3) | 243 (5.8) | 0.56 (0.45, 0.68) | <0.0001
CV death or Hospitalization for Heart Failure | 100 (2.2) | 138 (3.0) | 0.71 (0.55, 0.92) | 0.0089
Hospitalization for Heart Failure | 37 (0.8) | 71 (1.6) | 0.51 (0.34, 0.76)
All-Cause Mortality | 101 (2.2) | 146 (3.1) | 0.69 (0.53, 0.88) | 0.0035
N=Number of patients, CI=Confidence interval, CV=Cardiovascular, ESKD=End stage kidney disease.
NOTE: Time to first event was analyzed in a Cox proportional hazards model. Event rates are presented as the number of subjects with event per 100 patient years of follow-up.
There were too few events of renal death to compute a reliable hazard ratio.

Figure 6: Time to First Occurrence of the Primary Composite Endpoint, ≥50% Sustained Decline in eGFR, ESKD, CV or Renal Death (DAPA-CKD Study)

Patients at risk is the number of subjects at risk at the beginning of the period. 1 month corresponds to 30 days. 2-sided p-value is displayed. HR, CI and p-value are from the Cox proportional hazard model.

HR=hazard ratio; CI=confidence interval; eGFR=estimated glomerular filtration rate; ESKD=end stage kidney disease; CV=cardiovascular; vs=versus.

The results of the primary composite endpoint were consistent across the subgroups examined, including CKD patients with and without type 2 diabetes mellitus, causes of CKD, age, biological sex, race, UACR, and eGFR.

DAPA-CKD enrolled a population with relatively advanced CKD at high risk of progression. Exploratory analyses of a randomized, double-blind, placebo-controlled trial conducted to determine the effect of FARXIGA on CV outcomes (the DECLARE trial) support the conclusion that FARXIGA is also likely to be effective in patients with less advanced CKD.

14.5 Heart Failure

The efficacy and safety of FARXIGA 10 mg were assessed independently in two Phase 3 trials in adult patients with heart failure.

Dapagliflozin And Prevention of Adverse outcomes in Heart Failure (DAPA-HF, NCT03036124) was an international, multicenter, randomized, double-blind, placebo-controlled trial in patients with heart failure [New York Heart Association (NYHA) functional class II-IV] with reduced ejection fraction [left ventricular ejection fraction (LVEF) 40% or less] to determine whether FARXIGA reduces the risk of cardiovascular death and hospitalization for heart failure. Of 4744 patients, 2373 were randomized to FARXIGA 10 mg and 2371 to placebo and were followed for a median of 18 months.

Dapagliflozin Evaluation to Improve the LIVEs of Patients with PReserved Ejection Fraction Heart Failure (DELIVER, NCT03619213) was an international, multicenter, randomized, double-blind, placebo-controlled trial in patients aged ≥40 years with heart failure (NYHA class II-IV) with LVEF >40% and evidence of structural heart disease to determine whether FARXIGA reduces the risk of cardiovascular death, hospitalization for heart failure or urgent heart failure visits. Of 6263 patients, 3131 were randomized to FARXIGA 10 mg and 3132 to placebo and were followed for a median of 28 months. The trial included 654 (10%) heart failure patients who were randomized during hospitalization for heart failure or within 30 days of discharge.

In DAPA-HF, at baseline, 94% of patients were treated with ACEi, ARB or angiotensin receptor-neprilysin inhibitor (ARNI, including sacubitril/valsartan 11%), 96% with beta-blocker, 71% with mineralocorticoid receptor antagonist (MRA), 93% with diuretic, and 26% had an implantable device (with defibrillator function).

In DELIVER, at baseline, 77% of patients were treated with ACEi, ARB or ARNI, 83% with beta-blocker, 43% with MRA, 98% with diuretic.

In both trials, FARXIGA reduced the incidence of the primary composite endpoint of CV death, hospitalization for heart failure or urgent heart failure visit (see Table 17).

Table 17: Treatment Effect for the Primary Composite Endpoint [Full analysis set.] , its Components in the DAPA-HF and DELIVER Trials
 | DAPA-HF Trial |  |  |  | DELIVER Trial
 | Patients with events (event rate) |  | Hazard ratio (95% CI) | p-value [Two-sided p-values.] | Patients with events (event rate) |  | Hazard ratio (95% CI) | p-value
Efficacy Variable; (Time to first occurrence) | FARXIGA 10 mg N=2373 | Placebo N=2371 | Hazard ratio (95% CI) | p-value [Two-sided p-values.] | FARXIGA 10 mg N=3131 | Placebo N=3132 | Hazard ratio (95% CI) | p-value
Composite of Hospitalization for Heart Failure, CV Death [In DAPA-HF, the CV death component of the primary endpoint included death of undetermined cause. In DELIVER, the CV death component of the primary endpoint excluded death of undetermined cause.] or Urgent Heart Failure Visit | 386 (11.6) | 502 (15.6) | 0.74 (0.65, 0.85) | <0.0001 | 512 (7.8) | 610 (9.6) | 0.82 (0.73, 0.92) | 0.0008
Components of the composite endpoints
CV Death | 227 (6.5) | 273 (7.9) | 0.82 (0.69, 0.98) |  | 231 (3.3) | 261 (3.8) | 0.88 (0.74, 1.05)
Hospitalization for Heart Failure or Urgent Heart Failure Visit | 237 (7.1) | 326 (10.1) | 0.70 (0.59, 0.83) |  | 368 (5.6) | 455 (7.2) | 0.79 (0.69, 0.91)
Hospitalization for Heart Failure | 231 (6.9) | 318 (9.8) | 0.70 (0.59, 0.83) |  | 329 (5.0) | 418 (6.5) | 0.77 (0.67, 0.89)
Urgent Heart Failure Visit | 10 (0.3) | 23 (0.7) | 0.43 (0.20, 0.90) |  | 60 (0.9) | 78 (1.1) | 0.76 (0.55, 1.07)
N=Number of patients, CI=Confidence interval, CV=Cardiovascular.

NOTE: Time to first event was analyzed in a Cox proportional hazards model. The number of first events for the single components are the actual number of first events for each component and does not add up to the number of events in the composite endpoint. Event rates are presented as the number of subjects with event per 100 patient years of follow-up.

In both trials, all three components of the primary composite endpoint individually contributed to the treatment effect. In both trials, the FARXIGA and placebo event curves separated early and continued to diverge over the trial period (see Figures 7 and 9).

Figure 7: Time to the First Occurrence of the Composite of Cardiovascular Death*, Hospitalization for Heart Failure or Urgent Heart Failure Visit

A) DAPA-HF Trial

B) DELIVER Trial

NOTE: An urgent heart failure visit was defined as an urgent, unplanned, assessment by a physician, e.g., in an Emergency Department, and requiring treatment for worsening heart failure (other than just an increase in oral diuretics).

* In DAPA-HF, the CV death component of the primary endpoint included death of undetermined cause. In DELIVER, the CV death component of the primary endpoint excluded death of undetermined cause.

† Patients at risk is the number of patients at risk at the beginning of the period.

HR=Hazard ratio, CI=Confidence interval, CV=Cardiovascular.

Figure 8: Time to Cardiovascular Death*

A) DAPA-HF Trial

B) DELIVER Trial

* In DAPA-HF, the CV death component of the primary endpoint included death of undetermined cause. In DELIVER, the CV death component of the primary endpoint excluded death of undetermined cause.

† Patients at risk is the number of patients at risk at the beginning of the period.

HR=Hazard ratio, CI=Confidence interval, CV=Cardiovascular.

Figure 9: Time to the First Occurrence of Hospitalization for Heart Failure or Urgent Heart Failure Visit

A) DAPA-HF Trial

B) DELIVER Trial

* Patients at risk is the number of patients at risk at the beginning of the period.

HR=Hazard ratio, CI=Confidence interval.

In DAPA-HF, FARXIGA reduced the total number of hospitalizations for heart failure (first and recurrent) events and CV death, with 567 and 742 total events in the FARXIGA-treated vs placebo group (Rate Ratio 0.75 [95% CI 0.65, 0.88]; p=0.0002).

In DELIVER, FARXIGA reduced the total number of heart failure events (first and recurrent hospitalization for heart failure or urgent heart failure visit) and CV death, with 815 and 1057 total events in the FARXIGA treated vs placebo group (Rate Ratio 0.77 [95% CI 0.67, 0.89]; p=0.0003).

In both trials, the results of the primary composite endpoint were consistent across the subgroups examined (see Figure 10).

Figure 10: Treatment Effects for Primary Composite Endpoint (Cardiovascular Death and Heart Failure Events) Subgroup Analysis

A) DAPA-HF Trial

a Hazard ratio estimates are not presented for subgroups with less than 15 events in total, both arms combined.

n/N# Number of subjects with event/number of subjects in the subgroup.

NT-proBNP = N-terminal pro b-type natriuretic peptide, HF = Heart failure, MRA = mineralocorticoid receptor antagonist,

ECG = electrocardiogram, eGFR = estimated glomerular filtration rate.

Note: The figure above presents effects in various subgroups, all of which are baseline characteristics. The 95% confidence limits that are shown do not take into account the number of comparisons made and may not reflect the effect of a particular factor after adjustment for all other factors. Apparent homogeneity or heterogeneity among groups should not be over-interpreted.

B) DELIVER Trial

a Subacute patient defined as randomized during hospitalization for heart failure or within 30 days of discharge.

b Defined as history of type 2 diabetes mellitus. This analysis does not include type 2 diabetes mellitus as a stratification factor.

n/N# Number of subjects with event/number of subjects in the subgroup.

NT-proBNP = N-terminal pro b-type natriuretic peptide, HF = Heart failure, ECG = electrocardiogram, eGFR = estimated glomerular filtration rate, BMI = body mass index, SBP = systolic blood pressure, T2DM = type 2 diabetes mellitus.

NOTE: The figure above presents effects in various subgroups, all of which are baseline characteristics. The 95% confidence limits that are shown do not take into account the number of comparisons made and may not reflect the effect of a particular factor after adjustment for all other factors. Apparent homogeneity or heterogeneity among groups should not be over-interpreted.

The treatment effect of FARXIGA on the composite endpoint of cardiovascular death, hospitalization for heart failure or urgent heart failure was consistent across the LVEF range as evaluated in DAPA-HF and DELIVER trials (Figure 11).

Figure 11: Treatment Effects for Primary Composite Endpoint (Cardiovascular Death and Heart Failure Events) by LVEF (DAPA-HF and DELIVER Trials)

* 1 patient in DAPA-HF trial had LVEF >40. 4 patients in DELIVER trial had LVEF≤40.

In DAPA-HF trial, the 5% and 95% percentiles of LVEF were 20 and 40 respectively. In DELIVER trial, the 5% and 95% percentiles of LVEF were 42 and 70, respectively.

16 HOW SUPPLIED/STORAGE AND HANDLING

How Supplied

FARXIGA (dapagliflozin) tablets have markings on both sides and are available in the strengths and packages listed in Table 19.

Table 18: FARXIGA Tablet Presentations
Tablet Strength | Film-Coated Tablet Color/Shape | Tablet Markings | Package Size | NDC Code
5 mg | yellow, biconvex, round | “5” engraved on one side and “1427” engraved on the other side | Bottles of 30 | 0310-6205-30
5 mg | yellow, biconvex, round | “5” engraved on one side and “1427” engraved on the other side | Bottles of 90 | 0310-6205-90
10 mg | yellow, biconvex, diamond-shaped | “10” engraved on one side and “1428” engraved on the other side | Bottles of 30 | 0310-6210-30
10 mg | yellow, biconvex, diamond-shaped | “10” engraved on one side and “1428” engraved on the other side | Bottles of 90 | 0310-6210-90
10 mg | yellow, biconvex, diamond-shaped | “10” engraved on one side and “1428” engraved on the other side | Hospital Unit Dose Blister Pack:; Carton containing 30 tablets (3 blister cards x 10 tablets per card) | 0310-6210-39

Storage and Handling

Store at 20°C to 25°C (68°F to 77°F); excursions permitted between 15°C and 30°C (59°F and 86°F) [see USP Controlled Room Temperature].

17 PATIENT COUNSELING INFORMATION

Advise the patient to read the FDA-approved patient labeling (Medication Guide).

Diabetic Ketoacidosis in Patients with Type 1 Diabetes Mellitus and Other Ketoacidosis

In patients with type 1 diabetes mellitus, inform them that using FARXIGA can increase their risk of life-threatening diabetic ketoacidosis. For all other patients, inform them that FARXIGA can cause potentially fatal ketoacidosis and that type 2 diabetes mellitus and pancreatic disorders (e.g., history of pancreatitis or pancreatic surgery) are risk factors.

Educate all patients on precipitating factors (such as insulin dose reduction or missed insulin doses, infection, reduced caloric intake, ketogenic diet, surgery, dehydration, and alcohol abuse) and symptoms of ketoacidosis (including nausea, vomiting, abdominal pain, tiredness, and labored breathing). Inform patients that blood glucose may be normal even in the presence of ketoacidosis.

Advise patients that they may be asked to monitor ketones. If symptoms of ketoacidosis occur, instruct patients to discontinue FARXIGA and seek medical attention immediately [see Warnings and Precautions (5.1)].

Volume Depletion

Inform patients that symptomatic hypotension may occur with FARXIGA and advise them to contact their healthcare provider if they experience such symptoms [see Warnings and Precautions (5.2)]. Inform patients that dehydration may increase the risk for hypotension, and to have adequate fluid intake.

Serious Urinary Tract Infections

Inform patients of the potential for urinary tract infections, which may be serious. Provide them with information on the symptoms of urinary tract infections. Advise them to seek medical advice promptly if such symptoms occur [see Warnings and Precautions (5.3)].

Hypoglycemia with Concomitant Use with Insulin and Insulin Secretagogues

Inform patients that the incidence of hypoglycemia may increase when FARXIGA is added to an insulin secretagogue (e.g., sulfonylurea) and/or insulin. Educate patients on the signs and symptoms of hypoglycemia [see Warnings and Precautions (5.4)].

Necrotizing Fasciitis of the Perineum (Fournier’s Gangrene)

Inform patients that necrotizing infections of the perineum (Fournier’s Gangrene) have occurred with FARXIGA in patients with diabetes mellitus. Counsel patients to promptly seek medical attention if they develop pain or tenderness, redness, or swelling of the genitals or the area from the genitals back to the rectum, along with a fever above 100.4°F or malaise [see Warnings and Precautions (5.5)].

Genital Mycotic Infections in Females (e.g., Vulvovaginitis)

Inform female patients that vaginal yeast infections may occur and provide them with information on the signs and symptoms of vaginal yeast infections. Advise them of treatment options and when to seek medical advice [see Warnings and Precautions (5.6)].

Genital Mycotic Infections in Males (e.g., Balanitis)

Inform male patients that yeast infections of the penis (e.g., balanitis or balanoposthitis) may occur, especially in patients with prior history. Provide them with information on the signs and symptoms of balanitis and balanoposthitis (rash or redness of the glans or foreskin of the penis). Advise them of treatment options and when to seek medical advice [see Warnings and Precautions (5.6)].

Hypersensitivity Reactions

Inform patients that serious hypersensitivity reactions (e.g., urticaria, anaphylactic reactions, and angioedema) have been reported with FARXIGA. Advise patients to immediately report any signs or symptoms suggesting allergic reaction or angioedema, and to take no more of the drug until they have consulted prescribing physicians.

Pregnancy

Advise pregnant patients of the potential risk to a fetus with treatment with FARXIGA. Instruct patients to immediately inform their healthcare provider if pregnant or planning to become pregnant [see Use in Specific Populations (8.1)].

Lactation

Advise patients that use of FARXIGA is not recommended while breastfeeding [see Use in Specific Populations (8.2)].

Laboratory Tests

Due to its mechanism of action, patients taking FARXIGA will test positive for glucose in their urine.

Missed Dose

If a dose is missed, advise patients to take it as soon as it is remembered unless it is almost time for the next dose, in which case patients should skip the missed dose and take the medicine at the next regularly scheduled time. Advise patients not to take two doses of FARXIGA at the same time.

Distributed by:
AstraZeneca Pharmaceuticals LP
Wilmington, DE 19850

FARXIGA® is a registered trademark of the AstraZeneca group of companies.

MEDICATION GUIDE
FARXIGA® [FAR-SEE-GUH]
(dapagliflozin)
tablets, for oral use

What is the most important information I should know about FARXIGA?

FARXIGA can cause serious side effects, including:

- Diabetic ketoacidosis (increased ketones in your blood or urine) in people with type 1 diabetes and other ketoacidosis. FARXIGA can cause ketoacidosis that can be life-threatening and may lead to death. Ketoacidosis is a serious condition which needs to be treated in a hospital. People with type 1 diabetes have a high risk of getting ketoacidosis. People with type 2 diabetes or pancreas problems also have an increased risk of getting ketoacidosis. Ketoacidosis can also happen in people who: are sick, cannot eat or drink as usual, skip meals, are on a diet high in fat and low in carbohydrates (ketogenic diet), take less than the usual amount of insulin or miss insulin doses, drink too much alcohol, have a loss of too much fluid from the body (volume depletion), or who have surgery. Ketoacidosis can happen even if your blood sugar is less than 250 mg/dL. Your healthcare provider may ask you to periodically check ketones in your urine or blood.
  Stop taking FARXIGA and call your healthcare provider or get medical help right away if you get any of the following. If possible, check for ketones in your urine or blood, even if your blood sugar is less than 250 mg/dL.

- nausea
- vomiting
- stomach area (abdominal) pain

- tiredness
- trouble breathing
- ketones in your urine or blood

- Dehydration. FARXIGA can cause some people to become dehydrated (the loss of body water and salt). Dehydration may cause you to feel dizzy, faint, lightheaded, or weak, especially when you stand up (orthostatic hypotension). There have been reports of sudden kidney injury in people with Type 2 diabetes who are taking FARXIGA. You may be at a higher risk of dehydration if you:
  ∘ take medicines to lower your blood pressure, including water pills (diuretics)
  ∘ are on a low salt diet
  ∘ have kidney problems
  ∘ are 65 years of age or older
Talk to your healthcare provider about what you can do to prevent dehydration including how much fluid you should drink on a daily basis. Call your healthcare provider right away if you reduce the amount of food or liquid you drink, for example if you cannot eat or you start to lose liquids from your body, for example from vomiting, diarrhea, or being in the sun too long.
- Vaginal yeast infection. Women who take FARXIGA may get vaginal yeast infections. Symptoms of a vaginal yeast infection include:
  ∘ vaginal odor
  ∘ white or yellowish vaginal discharge (discharge may be lumpy or look like cottage cheese)
  ∘ vaginal itching
- Yeast infection of the penis (balanitis). Swelling of an uncircumcised penis may develop that makes it difficult to pull back the skin around the tip of the penis. Other symptoms of yeast infection of the penis include:
  ∘ redness, itching, or swelling of the penis
  ∘ foul smelling discharge from the penis
  ∘ rash of the penis
  ∘ pain in the skin around the penis

Talk to your healthcare provider about what to do if you get symptoms of a yeast infection of the vagina or penis. Your healthcare provider may suggest you use an over-the-counter antifungal medicine. Talk to your healthcare provider right away if you use an over-the-counter antifungal medication and your symptoms do not go away.

What is FARXIGA?

- FARXIGA is a prescription medicine used:
  ∘ to reduce the risk of further worsening of your kidney disease, end-stage kidney disease (ESKD), death due to cardiovascular disease, and hospitalization for heart failure in adults with chronic kidney disease
  ∘ to reduce the risk of cardiovascular death, hospitalization for heart failure and urgent heart failure visit in adults with heart failure, when the heart cannot pump enough blood to the rest of your body
  ∘ to reduce the risk of hospitalization for heart failure in adults with type 2 diabetes who also have known cardiovascular disease or multiple cardiovascular risk factors
  ∘ along with diet and exercise to improve blood sugar (glucose) control in adults and children who are 10 years of age and older with type 2 diabetes.
- FARXIGA is not for use to improve blood sugar (glucose) control in people with type 1 diabetes.
- FARXIGA is not for use to improve blood sugar (glucose) control in people with type 2 diabetes who have moderate to severe kidney problems, because it may not work.
- FARXIGA is not for people with certain genetic forms of polycystic kidney disease, or who are taking or have recently received immunosuppressive therapy to treat kidney disease. FARXIGA is not expected to work if you have these conditions.
- It is not known if FARXIGA is safe and effective to lower blood sugar (glucose) in children younger than 10 years of age with type 2 diabetes.
- It is not known if FARXIGA is safe and effective for treatment of heart failure or chronic kidney disease in children younger than 18 years of age.

Who should not take FARXIGA?

Do not take FARXIGA if you:

- are allergic to dapagliflozin or any of the ingredients in FARXIGA. See the end of this Medication Guide for a list of ingredients in FARXIGA. Symptoms of a serious allergic reaction to FARXIGA may include:
  ∘ rash
  ∘ raised red patches on your skin (hives)
  ∘ swelling of the face, lips, tongue, and throat that may cause difficulty in breathing or swallowing
If you have any of these symptoms, stop taking FARXIGA and contact your healthcare provider or go to the nearest hospital emergency room right away.

What should I tell my healthcare provider before taking FARXIGA?

Before you take FARXIGA, tell your healthcare provider if you:

- have type 1 diabetes or have had diabetic ketoacidosis.
- have a decrease in your insulin dose.
- have a serious infection.
- have a history of infection of the vagina or penis.
- have liver problems.
- have a history of urinary tract infections or problems with urination.
- are on a low sodium (salt) diet. Your healthcare provider may ask you to change your diet.
- are going to have surgery. Your healthcare provider may stop your FARXIGA before you have surgery. Talk to your healthcare provider if you are having surgery about when to stop taking FARXIGA and when to start it again.
- are eating less or there is a change in your diet.
- are dehydrated.
- have or have had problems with your pancreas, including pancreatitis or surgery on your pancreas.
- drink alcohol very often or drink a lot of alcohol in the short term (“binge” drinking).
- Are pregnant or plan to become pregnant. FARXIGA may harm your unborn baby. If you become pregnant while taking FARXIGA, your healthcare provider may switch you to a different medicine to control your blood sugar. Talk to your healthcare provider about the best way to control your blood sugar if you plan to become pregnant or while you are pregnant.
- are breastfeeding or plan to breastfeed. It is not known if FARXIGA passes into your breast milk. You should not breastfeed if you take FARXIGA.

Tell your healthcare provider about all the medicines you take, including prescription and over-the-counter medicines, vitamins, and herbal supplements.

FARXIGA may affect the way other medicines work, and other medicines may affect how FARXIGA works.

Know the medicines you take. Keep a list of them to show your healthcare provider and pharmacist when you get a new medicine.

How should I take FARXIGA?

- Take FARXIGA exactly as your healthcare provider tells you to take it.
- Take FARXIGA by mouth 1 time each day, with or without food.
- Your healthcare provider will tell you how much FARXIGA to take and when to take it. Your healthcare provider may change your dose if needed.
- If you miss a dose, take it as soon as you remember. If it is almost time for your next dose, skip the missed dose and take the medicine at the next regularly scheduled time. Do not take 2 doses of FARXIGA at the same time. Talk with your healthcare provider if you have questions about a missed dose.
- If you take too much FARXIGA, call your healthcare provider or Poison Help line at 1-800-222-1222, or go to the nearest emergency room right away.
- If you have diabetes:
  ∘ When your body is under some types of stress, such as fever, trauma (such as a car accident), infection, or surgery, the amount of diabetes medicine you need may change. Tell your healthcare provider right away if you have any of these conditions and follow your healthcare provider’s instructions.
  ∘ Your healthcare provider may tell you to take FARXIGA along with other diabetes medicines. Low blood sugar can happen more often when FARXIGA is taken with certain other diabetes medicines. See “What are the possible side effects of FARXIGA?”
- FARXIGA will cause your urine to test positive for glucose.
- Your healthcare provider may do certain blood tests before you start FARXIGA and during treatment as needed. Your healthcare provider may change your dose of FARXIGA based on the results of your blood tests.

What are the possible side effects of FARXIGA?

FARXIGA may cause serious side effects, including:

See “What is the most important information I should know about FARXIGA?”.

- Serious urinary tract infections. Serious urinary tract infections that may lead to hospitalization have happened in people who are taking FARXIGA. Tell your healthcare provider if you have any signs or symptoms of a urinary tract infection such as a burning feeling when passing urine, a need to urinate often, the need to urinate right away, pain in the lower part of your stomach (pelvis), or blood in the urine. Sometimes people also may have a fever, back pain, nausea or vomiting.
- Low blood sugar (hypoglycemia) in patients with diabetes mellitus. If you take FARXIGA with another medicine that can cause low blood sugar, such as a sulfonylurea or insulin, your risk of getting low blood sugar is higher. The dose of your sulfonylurea medicine or insulin may need to be lowered while you take FARXIGA. Signs and symptoms of low blood sugar may include:

  ∘ headache
  ∘ confusion
  ∘ hunger
  ∘ shaking or feeling jittery

∘ drowsiness
∘ dizziness
∘ fast heartbeat

∘ weakness
∘ sweating
∘ irritibility

- A rare but serious bacterial infection that causes damage to the tissue under the skin (necrotizing fasciitis) in the area between and around the anus and genitals (perineum). Necrotizing fasciitis of the perineum has happened in women and men with diabetes mellitus who take FARXIGA. Necrotizing fasciitis of the perineum may lead to hospitalization, may require multiple surgeries, and may lead to death. Seek medical attention right away if you have fever or you are feeling very weak, tired, or uncomfortable (malaise) and you develop any of the following symptoms in the area between and around the anus and genitals:

  ∘ pain or tenderness

∘ swelling

∘ redness of skin (erythema)

- Serious allergic reaction. If you have any symptoms of a serious allergic reaction, stop taking FARXIGA and call your healthcare provider right away or go to the nearest hospital emergency room. See “Who should not take FARXIGA?”. Your healthcare provider may give you a medicine for your allergic reaction and prescribe a different medicine for your diabetes.

The most common side effects of FARXIGA include:

- vaginal yeast infections and yeast infections of the penis
- stuffy or runny nose and sore throat
- changes in urination, including urgent need to urinate more often, in larger amounts, or at night

These are not all the possible side effects of FARXIGA. For more information, ask your healthcare provider or pharmacist.

Call your doctor for medical advice about side effects. You may report side effects to FDA at 1-800-FDA-1088.

How should I store FARXIGA?

Store FARXIGA at room temperature between 68°F and 77°F (20°C and 25°C).

General information about the safe and effective use of FARXIGA

Medicines are sometimes prescribed for purposes other than those listed in a Medication Guide. Do not use FARXIGA for a condition for which it is not prescribed. Do not give FARXIGA to other people, even if they have the same symptoms you have. It may harm them.

This Medication Guide summarizes the most important information about FARXIGA. If you would like more information, talk to your healthcare provider. You can ask your pharmacist or healthcare provider for information about FARXIGA that is written for healthcare professionals.

For more information about FARXIGA, go to www.farxiga.com or call 1-800-236-9933.

What are the ingredients in FARXIGA?

Active ingredient: dapagliflozin.

Inactive ingredients: anhydrous lactose, crospovidone, magnesium stearate, microcrystalline cellulose, and silicon dioxide. The film coating contains: polyethylene glycol, polyvinyl alcohol, talc, titanium dioxide, and yellow iron oxide.

Distributed by: AstraZeneca Pharmaceuticals LP Wilmington, DE 19850

FARXIGA is a registered trademark of the AstraZeneca group of companies.

This Medication Guide has been approved by the U.S. Food and Drug Administration. Revised 06/2024

PRINCIPAL DISPLAY PANEL – 5 mg tablets

30 Tablets NDC 0310-6205-30
farxiga®
(dapagliflozin) tablets
5 mg
Dispense with
Medication Guide
Rx only
AstraZeneca

PRINCIPAL DISPLAY PANEL – 10 mg tablets

30 Tablets NDC 0310-6210-30
farxiga®
(dapagliflozin) tablets
10 mg
Dispense with
Medication Guide
Rx only
AstraZeneca